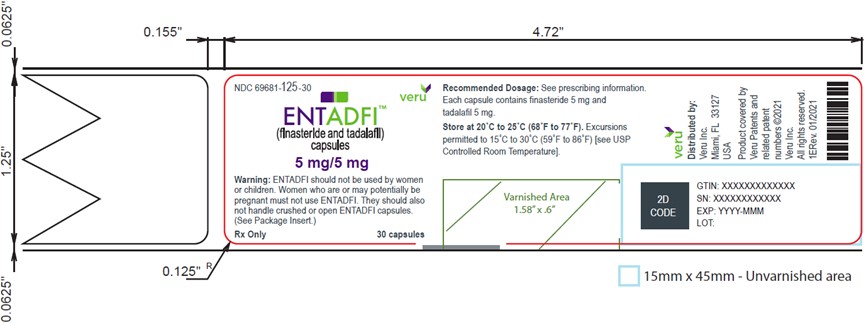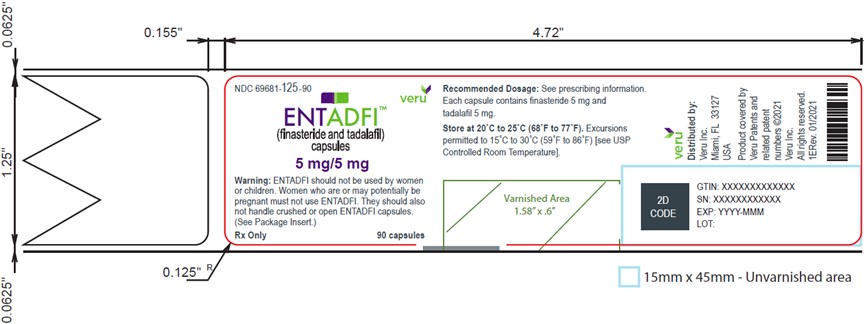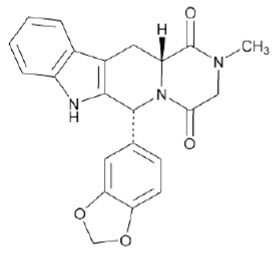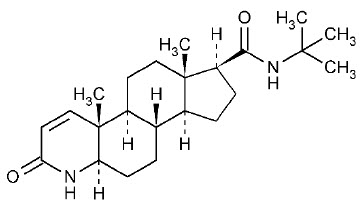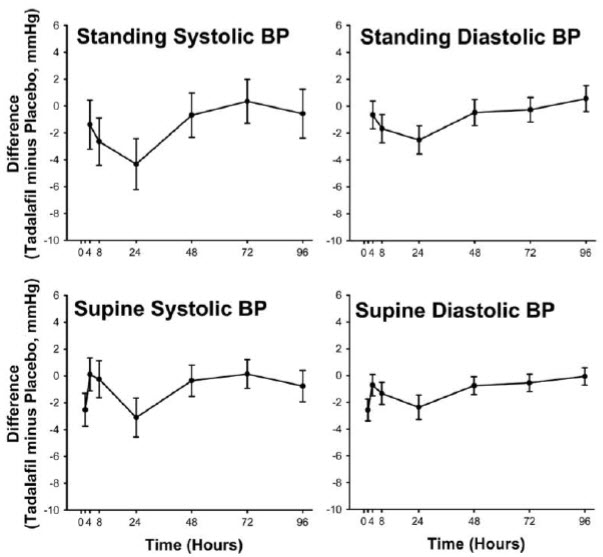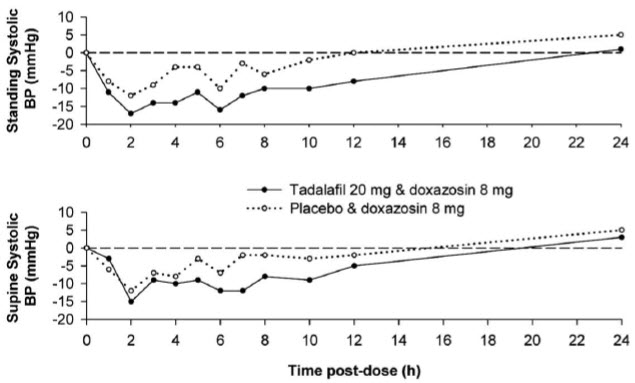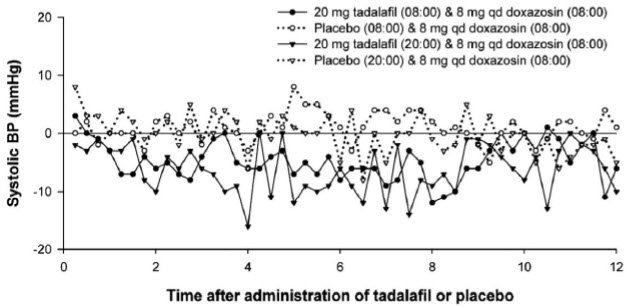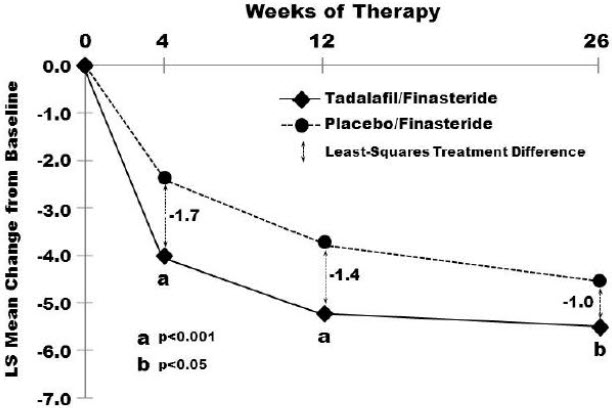 DRUG LABEL: ENTADFI
NDC: 69681-125 | Form: CAPSULE
Manufacturer: Veru Inc.
Category: prescription | Type: HUMAN PRESCRIPTION DRUG LABEL
Date: 20230112

ACTIVE INGREDIENTS: tadalafil 5 mg/1 1; finasteride 5 mg/1 1
INACTIVE INGREDIENTS: LACTOSE MONOHYDRATE; SODIUM STARCH GLYCOLATE TYPE A; SODIUM LAURYL SULFATE; MICROCRYSTALLINE CELLULOSE; SILICON DIOXIDE; MAGNESIUM STEARATE; CARRAGEENAN; HYPROMELLOSE, UNSPECIFIED; potassium chloride; TITANIUM DIOXIDE

HIGHLIGHTS OF PRESCRIBING INFORMATION

These highlights do not include all the information needed to use ENTADFI safely and effectively. See full prescribing information for ENTADFI.
ENTADFI™ (finasteride and tadalafil) capsules, for oral use
Initial U.S. Approval: 2021

1 INDICATIONS AND USAGE

ENTADFI is a combination of finasteride, a 5α-reductase inhibitor, and tadalafil, a phosphodiesterase 5 (PDE5) inhibitor, and, indicated to initiate treatment of the signs and symptoms of benign prostatic hyperplasia (BPH) in men with an enlarged prostate for up to 26 weeks. (1)

2 DOSAGE AND ADMINISTRATION

One capsule orally once daily at approximately the same time every day for up to 26 weeks. Take without food. (2)

3 DOSAGE FORMS AND STRENGTHS

Capsules: fixed dose combination containing finasteride 5 mg and tadalafil 5 mg. (3)

4 CONTRAINDICATIONS

- Concomitant use with any form of organic nitrate, either regularly and/or intermittently. ENTADFI can potentiate the hypotensive effect of nitrates. (4)
- Known hypersensitivity to ENTADFI or any of its components. (4)
- Pregnancy. (4)
- Concomitant use with guanylate cyclase (GC) stimulators. ENTADFI may potentiate the hypotensive effects of GC stimulators. (4)

5 WARNINGS AND PRECAUTIONS

- Cardiovascular Risk: Administer nitrates concomitantly only in life-threatening situations under close medical supervision. (5.1)
- Potential for Drug Interactions when taking ENTADFI: Use alpha-blockers, antihypertensives, strong CYP3A4 inhibitors and alcohol with caution due to the potential for symptomatic hypotension. (5.2), (5.3), (5.12)
- Consideration of Other Urological Conditions Prior to Initiation of Treatment for BPH: Carefully monitor patients with large residual urinary volume and/or severely diminished urinary flow for obstructive uropathy. Prostate cancer and BPH may coexist. (5.4)
- Effects of PSA and the Use of PSA in Prostate Cancer Detection: PSA reduction by approximately 50% within six months of treatment can be seen which can affect interpretation of serial and isolated PSA values. Evaluate any confirmed increase in PSA as it may signal the presence of prostate cancer. (5.5)
- Increased Risk of High-Grade Prostate Cancer: Increased incidence of high-grade prostate cancer has been observed. (5.6)
- Risk to Male Fetus from Topical ENTADFI Exposure to Pregnant Females: Pregnant women should not handle crushed or open ENTADFI capsules. (5.7)
- Hypersensitivity Reactions: Immediately discontinue if a hypersensitivity reaction occurs. (5.8)
- Prolonged Erection and Priapism: Use with caution in patients predisposed to priapism. Advise patients to seek emergency treatment if an erection lasts more than 4 hours. (5.9)
- Ocular Adverse Reactions: Stop use in the event of a sudden loss of vision in one or both eyes. Such an event may be a sign of non-arteritic anterior ischemic optic neuropathy (NAION). Use with caution in patients at increased risk of NAION. (5.10)
- Sudden Hearing Loss: Stop use and seek prompt medical attention. (5.11)

6 ADVERSE REACTIONS

Most common adverse reactions associated with finasteride monotherapy (≥1%) in a 4-year study were impotence, decreased libido, decreased volume of ejaculate, breast enlargement, breast tenderness, and rash (6.1).

Most common adverse reactions (≥2%) associated with tadalafil were headache, dyspepsia, back pain, myalgia, nasal congestion, flushing, and pain in limb (6.1).

To report SUSPECTED ADVERSE REACTIONS, contact Veru Inc. at 1-866-936-8233 or www.verupharma.com or FDA at 1-800-FDA-1088 or www.fda.gov/medwatch.

7 DRUG INTERACTIONS

CYP3A4 inducers: Concomitant use may increase tadalafil exposure. Use is not recommended. (7.2)

8 USE IN SPECIFIC POPULATIONS

Hepatic Impairment:

- Child's Pugh Class A and B: Use with caution. (8.6)
- Child's Pugh Class C: Use is not recommended. (8.6)

Renal Impairment:

- Creatinine clearance less than 50 mL/min or hemodialysis: Use is not recommended. (8.7)

FULL PRESCRIBING INFORMATION

1 INDICATIONS AND USAGE

ENTADFI is indicated to initiate treatment of the signs and symptoms of benign prostatic hyperplasia (BPH) in men with an enlarged prostate for up to 26 weeks.

Limitations of Use
ENTADFI is not recommended for more than 26 weeks because the incremental benefit of tadalafil decreases from 4 weeks until 26 weeks, and the incremental benefit beyond 26 weeks is unknown [see Clinical Studies (14)].

2 DOSAGE AND ADMINISTRATION

The recommended dosage of ENTADFI is one capsule (containing finasteride 5 mg and tadalafil 5 mg) orally once daily at approximately the same time every day for up to 26 weeks.

Take ENTADFI on an empty stomach [see Clinical Pharmacology (12.3)].

3 DOSAGE FORMS AND STRENGTHS

Capsules: finasteride 5 mg and tadalafil 5 mg, in a size 3 capsule with a white opaque cap and body with black two line bars printed on the cap and on the body.

4 CONTRAINDICATIONS

ENTADFI is contraindicated in the following situations:

- Concomitant use of any form of organic nitrate, either regularly and/or intermittently. ENTADFI can potentiate the hypotensive effect of nitrates [see Warning and Precautions (5.1, 5.2) and Drug Interactions (7.1)].
- Patients with known hypersensitivity to finasteride, tadalafil, or to any of the components of ENTADFI. Hypersensitivity reactions have included Stevens-Johnson syndrome, exfoliative dermatitis, pruritis, urticaria, and angioedema [see Warnings and Precautions (5.8) and Adverse Reactions (6.2)].
- Pregnancy [see Warnings and Precautions (5.7) and Use in Specific Populations (8.1)].
- Concomitant use with a guanylate cyclase (GC) stimulator. ENTADFI may potentiate the hypotensive effects of GC stimulators [see Drug Interactions (7.1)].

5 WARNINGS AND PRECAUTIONS

5.1 Cardiovascular Risk

ENTADFI is contraindicated in patients taking any form of organic nitrate, either regularly and/or intermittently [see Contraindications (4)]. Discuss with patients the appropriate action in the event that they experience anginal chest pain requiring nitroglycerin following intake of ENTADFI. In such a patient, who has taken ENTADFI, where nitrate administration is deemed medically necessary for a life-threatening situation, at least 48 hours should have elapsed after the last dose of ENTADFI before nitrate administration is considered. In such circumstances, nitrates should still only be administered under close medical supervision with appropriate hemodynamic monitoring. Therefore, advise patients who experience anginal chest pain after taking ENTADFI to seek immediate medical attention [see Contraindications (4)].

Patients with left ventricular outflow obstruction, (e.g., aortic stenosis and idiopathic hypertrophic subaortic stenosis) can be sensitive to the action of vasodilators, including PDE5 inhibitors.

The following groups of patients with cardiovascular disease were not included in clinical safety and efficacy trials for tadalafil, and therefore until further information is available, ENTADFI is not recommended for the following groups of patients:

- myocardial infarction within the last 90 days
- unstable angina or angina occurring during sexual intercourse
- New York Heart Association Class 2 or greater heart failure in the last 6 months
- uncontrolled arrhythmias, hypotension (<90/50 mm Hg), or uncontrolled hypertension
- stroke within the last 6 months.

As with other PDE5 inhibitors, tadalafil, a component of ENTADFI, has mild systemic vasodilatory properties that may result in transient decreases in blood pressure. In a clinical pharmacology study, tadalafil 20 mg resulted in a mean maximal decrease in supine blood pressure, relative to placebo, of 1.6/0.8 mm Hg in healthy subjects [see Clinical Pharmacology (12.2)]. While this effect should not be of consequence in most patients, prior to prescribing ENTADFI, carefully consider whether patients with underlying cardiovascular disease could be affected adversely by such vasodilatory effects. Patients with severely impaired autonomic control of blood pressure may be particularly sensitive to the actions of vasodilators, including PDE5 inhibitors.

5.2 Potential for Drug Interactions when Taking ENTADFI

ENTADFI provides continuous plasma tadalafil levels. Consider this when evaluating the potential for ENTADFI interactions with medications (e.g., nitrates, alpha-blockers, anti-hypertensives and strong inhibitors of CYP3A4) and with substantial consumption of alcohol [see Drug Interactions (7)].

5.3 Concomitant Use with Alpha-blockers or Antihypertensives

Discuss with patients the potential for ENTADFI to augment the blood-pressure-lowering effect of alpha-blockers and antihypertensive medications [see Drug Interactions (7.1) and Clinical Pharmacology (12.2)].

Caution is advised when PDE5 inhibitors are coadministered with alpha-blockers. PDE5 inhibitors, including ENTADFI, and alpha-adrenergic blocking agents are both vasodilators with blood-pressure-lowering effects. When vasodilators are used in combination, an additive effect on blood pressure may be anticipated. In some patients, concomitant use of these two drug classes can lower blood pressure significantly [see Drug Interactions (7.2) and Clinical Pharmacology (12.2)], which may lead to symptomatic hypotension (e.g., fainting). Consider the following:

BPH

- The efficacy of the coadministration of an alpha-blocker and ENTADFI for the treatment of BPH has not been adequately studied, and due to the potential vasodilatory effects of combined use resulting in blood pressure lowering, the combination of ENTADFI and alpha-blockers is not recommended for the treatment of BPH [see Drug Interactions (7.2), and Clinical Pharmacology (12.2)].
- Discontinue alpha-blockers at least one day prior to starting ENTADFI for once daily use for the treatment of BPH.

5.4 Consideration of Other Urological Conditions Prior to Initiating Treatment for BPH

Prior to initiating treatment with ENTADFI for BPH, consider whether the patient has other urological conditions that may cause similar symptoms. In addition, prostate cancer and BPH may coexist.

Carefully monitor patients with large residual urinary volume and/or severely diminished urinary flow for obstructive uropathy. These patients may not be candidates for ENTADFI therapy.

5.5 Effects on Prostate Specific Antigen (PSA) and the Use of PSA in Prostate Cancer Detection

In clinical studies, finasteride, a component of ENTADFI, reduced serum PSA concentration by approximately 50% within six months of treatment. This decrease is predictable over the entire range of PSA values in patients with symptomatic BPH, although it may vary in individuals.

For interpretation of serial PSAs in men taking ENTADFI, a new PSA baseline should be established at least six months after starting treatment and PSA monitored periodically thereafter. Any confirmed increase from the lowest PSA value while on ENTADFI may signal the presence of prostate cancer and should be evaluated, even if PSA levels are still within the normal range for men not taking a 5α-reductase inhibitor. Non-compliance with ENTADFI therapy may also affect PSA test results. To interpret an isolated PSA value in patients treated with ENTADFI for six months or more, double the PSA values for comparison with normal ranges in untreated men. These adjustments preserve the utility of PSA to detect prostate cancer in men treated with ENTADFI.

ENTADFI may also cause decreases in serum PSA in the presence of prostate cancer.

The ratio of free to total PSA (percent free PSA) remains constant even under the influence of ENTADFI. If clinicians elect to use percent free PSA as an aid in the detection of prostate cancer in men undergoing ENTADFI therapy, no adjustment to its value appears necessary.

5.6 Increased Risk of High-Grade Prostate Cancer

Use of 5α-reductase inhibitors, including ENTADFI, may increase the risk of development of high-grade prostate cancer. Men aged 55 years and over with a normal digital rectal examination and PSA less than or equal to 3.0 ng/mL at baseline taking finasteride, a component of ENTADFI (5 mg daily) in the 7-year Prostate Cancer Prevention Trial (PCPT) had an increased risk of Gleason score 8 to 10 prostate cancer (finasteride 1.8% vs placebo 1.1%) [See Adverse Reactions (6.1)]. Similar results were observed in a 4-year placebo-controlled clinical trial with a different 5α-reductase inhibitor. Whether the effect of 5α-reductase inhibitors to reduce prostate volume, or study-related factors, impacted the results of these studies has not been established.

5.7 Risk to Male Fetus from Topical ENTADFI Exposure to Pregnant Females

ENTADFI is contraindicated in pregnant females and is not indicated for use in females. Based on animal studies and the mechanism of action of finasteride, ENTADFI may cause abnormal development of external genitalia in a male fetus if administered to a pregnant female. Pregnant females should not handle crushed or open ENTADFI capsules because of the possibility of absorption of finasteride and the subsequent potential risk to a male fetus. If a pregnant female comes in contact with crushed or broken ENTADFI capsules, the contact area should be washed immediately with soap and water [see Contraindications (4), Use in Specific Populations (8.1)].

5.8 Hypersensitivity Reactions

ENTADFI is contraindicated in patients with a history of hypersensitivity reactions to finasteride, tadalafil, or to any component of ENTADFI [see Contraindications (4)]. Immediately discontinue ENTADFI if a hypersensitivity reaction occurs. Hypersensitivity reactions have included Stevens-Johnson syndrome, exfoliative dermatitis, pruritis, urticaria, and angioedema [see Adverse Reactions (6.2)].

5.9 Prolonged Erection and Priapism

Instruct patients who have an erection lasting greater than 4 hours, whether painful or not, to seek emergency medical attention. Use ENTADFI with caution in patients who have conditions that might predispose them to priapism (such as sickle cell anemia, multiple myeloma, or leukemia), or in patients with anatomical deformation of the penis (such as angulation, cavernosal fibrosis, or Peyronie's disease).

There have been rare reports of prolonged erections greater than 4 hours and priapism (painful erections greater than 6 hours in duration) for this class of compounds. Priapism, if not treated promptly, can result in irreversible damage to the erectile tissue.

5.10 Ocular Adverse Reactions

Advise patients to stop use of all phosphodiesterase type 5 (PDE5) inhibitors, including ENTADFI, and seek medical attention in the event of a sudden loss of vision in one or both eyes. Such an event may be a sign of non-arteritic anterior ischemic optic neuropathy (NAION), a rare condition and a cause of decreased vision, including permanent loss of vision, that has been reported rarely postmarketing in temporal association with the use of all PDE5 inhibitors. Based on published literature, the annual incidence of NAION is 2.5 to 11.8 cases per 100,000 in males aged 50 years and older.

Consider whether patients with underlying NAION risk factors could be adversely affected by use of PDE5 inhibitors. Individuals who have already experienced NAION are at increased risk of NAION recurrence. Therefore, use PDE5 inhibitors, including ENTADFI, with caution in these patients and only when the anticipated benefits outweigh the risks. Individuals with "crowded" optic disc are also considered at greater risk for NAION compared to the general population; however, evidence is insufficient to support screening of prospective users of PDE5 inhibitors, including ENTADFI, for this uncommon condition.

Patients with known hereditary degenerative retinal disorders, including retinitis pigmentosa, were not included in the clinical trials, and use of ENTADFI in these patients is not recommended.

An observational case-crossover study evaluated the risk of NAION when PDE5 inhibitor use, as a class, occurred immediately before NAION onset (within 5 half-lives), compared to PDE5 inhibitor use in a prior time period. The results suggest an approximate 2-fold increase in the risk of NAION, with a risk estimate of 2.15 (95% CI 1.06, 4.34). A similar study reported a consistent result, with a risk estimate of 2.27 (95% CI 0.99, 5.20). Other risk factors for NAION, such as the presence of "crowded" optic disc, may have contributed to the occurrence of NAION in these studies.

Neither the rare postmarketing reports, nor the association of PDE5 inhibitor use and NAION in the observational studies, substantiate a causal relationship between PDE5 inhibitor use and NAION [see Adverse Reactions (6.2)].

5.11 Sudden Hearing Loss

Advise patients to stop taking ENTADFI and seek prompt medical attention in the event of sudden decrease or loss of hearing. These events, which may be accompanied by tinnitus and dizziness, have been reported in temporal association to the intake of PDE5 inhibitors, including ENTADFI. It is not possible to determine whether these events are related directly to the use of PDE5 inhibitors, such as ENTADFI, or to other factors [see Adverse Reactions (6.1, 6.2)].

5.12 Concomitant Use with Alcohol

Inform patients that both alcohol and tadalafil, a PDE5 inhibitor and a component of ENTADFI, act as mild vasodilators. When mild vasodilators are taken in combination, blood-pressure-lowering effects of each individual compound may be increased. Inform patients that substantial consumption of alcohol (e.g., 5 units or greater) in combination with ENTADFI can increase the potential for orthostatic signs and symptoms, including increase in heart rate, decrease in standing blood pressure, dizziness, and headache [see Drug Interactions (7.3)].

5.13 Concomitant Use with Strong Inhibitors of Cytochrome P450 3A4 (CYP3A4)

Tadalafil, a component of ENTADFI, is metabolized predominantly by CYP3A4 in the liver. ENTADFI is not recommended in patients taking strong inhibitors of CYP3A4 [see Drug Interactions (7.1), Clinical Pharmacology (12.3)].

5.14 Effects on Bleeding

Studies in vitro have demonstrated that tadalafil, a component of ENTADFI, is a selective inhibitor of PDE5. PDE5 is found in platelets. When administered in combination with aspirin, tadalafil 20 mg did not prolong bleeding time, relative to aspirin alone. ENTADFI has not been administered to patients with bleeding disorders or significant active peptic ulceration. Although tadalafil, a component of ENTADFI, has not been shown to increase bleeding times in healthy subjects, use ENTADFI with caution in patients with bleeding disorders or significant active peptic ulceration after a careful risk-benefit assessment.

6 ADVERSE REACTIONS

6.1 Clinical Trials Experience

Because clinical trials are conducted under widely varying conditions, adverse reaction rates observed in the clinical trials of a drug cannot be directly compared to rates in the clinical trials of another drug and may not reflect the rates observed in practice.

The safety of ENTADFI is based on the following:

- Placebo controlled trials in which tadalafil was administered as monotherapy for the treatment of either BPH alone or BPH and a condition for which ENTADFI is not approved
- Placebo controlled trials in which finasteride was administered as monotherapy for the treatment of BPH

Finasteride:

4-Year Placebo-Controlled Study (PLESS)

In PLESS, 1524 patients treated with finasteride 5 mg once daily and 1516 patients treated with placebo were evaluated for safety over a period of 4 years. The most frequently reported adverse reactions were related to sexual function. 3.7% (57 patients) treated with finasteride and 2.1% (32 patients) treated with placebo discontinued therapy as a result of adverse reactions related to sexual function, which are the most frequently reported adverse reactions.

Table 1 presents the only clinical adverse reactions considered possibly, probably or definitely drug related by the investigator, for which the incidence on finasteride was ≥1% and greater than placebo over the 4 years of the study. In years 2-4 of the study, there was no significant difference between treatment groups in the incidences of impotence, decreased libido and ejaculation disorder.

Table 1: Drug-Related Adverse Reactions
 | Year 1 (%) |  | Years 2, 3 and 4 [Combined Years 2-4] (%)
 | Finasteride | Placebo | Finasteride | Placebo
Impotence | 8.1 | 3.7 | 5.1 | 5.1
Decreased Libido | 6.4 | 3.4 | 2.6 | 2.6
Decreased Volume of Ejaculate | 3.7 | 0.8 | 1.5 | 0.5
Ejaculation Disorder | 0.8 | 0.1 | 0.2 | 0.1
Breast Enlargement | 0.5 | 0.1 | 1.8 | 1.1
Breast Tenderness | 0.4 | 0.1 | 0.7 | 0.3
Rash | 0.5 | 0.2 | 0.5 | 0.1
N = 1524 and 1516, finasteride vs placebo, respectively

Phase III Studies and 5-Year Open Extensions

The adverse experience profile in the 1-year, placebo-controlled, Phase III studies, the 5-year open extensions, and PLESS were similar.

Medical Therapy of Prostatic Symptoms (MTOPS) Study

In the MTOPS study, 3047 men with symptomatic BPH were randomized to receive finasteride 5 mg once daily (n=768), doxazosin 4 or 8 mg once daily (n=756), the combination of finasteride 5 mg once daily and doxazosin 4 or 8 mg once daily (n=786), or placebo (n=737) for 4 to 6 years.

The incidence rates of drug-related adverse reactions reported by ≥ 2% of patients in any treatment group in the MTOPS Study are listed in Table 2.

The individual adverse reactions which occurred more frequently in the combination group compared to either drug alone were: asthenia, postural hypotension, peripheral edema, dizziness, decreased libido, rhinitis, abnormal ejaculation, impotence and abnormal sexual function (see Table 1). Of these, the incidence of abnormal ejaculation in patients receiving combination therapy was comparable to the sum of the incidences of this adverse experience reported for the two monotherapies.

Combination therapy with finasteride and doxazosin was associated with no new clinical adverse reactions.

Four patients in MTOPS reported the adverse reaction of breast cancer. Three of these patients were on finasteride only and one was on combination therapy. See Long-Term Data.

The MTOPS Study was not specifically designed to make statistical comparisons between groups for reported adverse reactions. In addition, direct comparisons of safety data between the MTOPS study and previous studies of the single agents may not be appropriate based upon differences in patient population, dosage or dose regimen, and other procedural and study design elements.

Table 2: Incidence ≥2% in One or More Treatment Groups Drug-Related Clinical Adverse Reactions in MTOPS
Adverse Reaction | Placebo (N=737) (%) | Doxazosin 4 mg or 8 mg [Doxazosin dose was achieved by weekly titration (1 to 2 to 4 to 8 mg). The final tolerated dose (4 mg or 8 mg) was administered at end-Week 4. Only those patients tolerating at least 4 mg were kept on doxazosin. The majority of patients received the 8-mg dose over the duration of the study.] (N=756) (%) | Finasteride (N=768) (%) | Combination (N=786) (%)
Body as a whole
Asthenia | 7.1 | 15.7 | 5.3 | 16.8
Headache | 2.3 | 4.1 | 2.0 | 2.3
Cardiovascular
Hypotension | 0.7 | 3.4 | 1.2 | 1.5
Postural Hypotension | 8.0 | 16.7 | 9.1 | 17.8
Metabolic and Nutritional
Peripheral Edema | 0.9 | 2.6 | 1.3 | 3.3
Nervous
Dizziness | 8.1 | 17.7 | 7.4 | 23.2
Libido Decreased | 5.7 | 7.0 | 10.0 | 11.6
Somnolence | 1.5 | 3.7 | 1.7 | 3.1
Respiratory
Dyspnea | 0.7 | 2.1 | 0.7 | 1.9
Rhinitis | 0.5 | 1.3 | 1.0 | 2.4
Urogenital
Abnormal Ejaculation | 2.3 | 4.5 | 7.2 | 14.1
Gynecomastia | 0.7 | 1.1 | 2.2 | 1.5
Impotence | 12.2 | 14.4 | 18.5 | 22.6
Sexual Function Abnormal | 0.9 | 2.0 | 2.5 | 3.1

Long-Term Data

High-Grade Prostate Cancer

The PCPT trial was a 7-year randomized, double-blind, placebo-controlled trial that enrolled 18,882 men ≥55 years of age with a normal digital rectal examination and a PSA ≤3.0 ng/mL. Men received either finasteride 5 mg or placebo daily. Patients were evaluated annually with PSA and digital rectal exams. Biopsies were performed for elevated PSA, an abnormal digital rectal exam, or the end of study. The incidence of Gleason score 8-10 prostate cancer was higher in men treated with finasteride (1.8%) than in those treated with placebo (1.1%) [see and Precautions (5.2)]. In a 4-year placebo-controlled clinical trial with another 5α-reductase inhibitor, similar results for Gleason score 8-10 prostate cancer were observed (1% vs 0.5% placebo).

No clinical benefit has been demonstrated in patients with prostate cancer treated with finasteride 5 mg.

Breast Cancer

During the 4- to 6-year placebo- and comparator-controlled MTOPS study that enrolled 3047 men, there were 4 cases of breast cancer in men treated with finasteride but no cases in men not treated with finasteride. During the 4-year, placebo-controlled PLESS study that enrolled 3040 men, there were 2 cases of breast cancer in placebo-treated men but no cases in men treated with finasteride. During the 7-year placebo-controlled Prostate Cancer Prevention Trial (PCPT) that enrolled 18,882 men, there was 1 case of breast cancer in men treated with finasteride, and 1 case of breast cancer in men treated with placebo. The relationship between long-term use of finasteride and male breast neoplasia is currently unknown.

Sexual Function

There is no evidence of increased sexual adverse reactions with increased duration of treatment with finasteride 5 mg. New reports of drug-related sexual adverse reactions decreased with duration of therapy.

Tadalafil:

The safety of tadalafil was evaluated in three placebo-controlled clinical trials of 12 weeks duration, in which tadalafil was administered as monotherapy at a dose of 5 mg orally once daily for the treatment of either BPH alone or BPH and a condition for which ENTADFI is not approved. The mean age of the patients was 63 years (range 44 to 93) and the discontinuation rate due to adverse reactions in patients treated with tadalafil was 3.6% compared to 1.6% in placebo-treated patients. Adverse reactions leading to discontinuation reported by at least 2 patients treated with tadalafil included headache, upper abdominal pain, and myalgia. The following adverse reactions were reported (see Table 3).

Table 3: Adverse Reactions Reported by ≥1% of Patients Treated with Tadalafil for Once Daily Use (5 mg) and More Frequent on Drug than Placebo in Three Placebo-Controlled Clinical Studies of 12 Weeks Treatment Duration
Adverse Reaction | Tadalafil 5 mg (N=581) | Placebo (N=576)
Headache | 4.1% | 2.3%
Dyspepsia | 2.4% | 0.2%
Back pain | 2.4% | 1.4%
Nasopharyngitis | 2.1% | 1.6%
Diarrhea | 1.4% | 1.0%
Pain in extremity | 1.4% | 0.0%
Myalgia | 1.2% | 0.3%
Dizziness | 1.0% | 0.5%

Additional, less frequent adverse reactions (<1%) reported in the controlled clinical trials of tadalafil for BPH or a different indication and BPH included: gastroesophageal reflux disease, upper abdominal pain, nausea, vomiting, arthralgia, and muscle spasm.

Back Pain

Back pain or myalgia was reported at incidence rates described in Table 3. In tadalafil clinical pharmacology trials, back pain or myalgia generally occurred 12 to 24 hours after dosing and typically resolved within 48 hours. The back pain/myalgia associated with tadalafil treatment was characterized by diffuse bilateral lower lumbar, gluteal, thigh, or thoracolumbar muscular discomfort and was exacerbated by recumbency. In general, pain was reported as mild or moderate in severity and resolved without medical treatment, but severe back pain was reported with a low frequency (<5% of all reports). When medical treatment was necessary, acetaminophen or non-steroidal anti-inflammatory drugs were generally effective; however, in a small percentage of subjects who required treatment, a mild narcotic (e.g., codeine) was used. In the 1-year open label extension study, back pain and myalgia were reported in 5.5% and 1.3% of patients, respectively. Diagnostic testing, including measures for inflammation, muscle injury, or renal damage revealed no evidence of medically significant underlying pathology. In studies of tadalafil for once daily use, adverse reactions of back pain and myalgia were generally mild or moderate with a discontinuation rate of <1% across all indications.

Across all studies with any tadalafil dose, changes in color vision were reported in <0.1% of patients.

The following section identifies additional events (<2%) reported in controlled clinical trials of tadalafil (a component of ENTADFI) including trials for an unapproved use of ENTADFI. A causal relationship of these events to tadalafil is uncertain. Excluded from this list are those events that were minor, those with no plausible relation to drug use, and reports too imprecise to be meaningful:

- Body as a Whole — asthenia, face edema, fatigue, pain, peripheral edema
- Cardiovascular — angina pectoris, chest pain, hypotension, myocardial infarction, postural hypotension, palpitations, syncope, tachycardia
- Digestive — abnormal liver function tests, dry mouth, dysphagia, esophagitis, gastritis, GGTP increased, loose stools, nausea, upper abdominal pain, vomiting, gastroesophageal reflux disease, hemorrhoidal hemorrhage, rectal hemorrhage
- Musculoskeletal — arthralgia, neck pain
- Nervous — dizziness, hypesthesia, insomnia, paresthesia, somnolence, vertigo
- Renal and Urinary — renal impairment
- Respiratory — dyspnea, epistaxis, pharyngitis
- Skin and Appendages — pruritus, rash, sweating
- Ophthalmologic — blurred vision, changes in color vision, conjunctivitis (including conjunctival hyperemia), eye pain, lacrimation increase, swelling of eyelids
- Otologic — sudden decrease or loss of hearing, tinnitus
- Urogenital — erection increased, spontaneous penile erection

6.2 Postmarketing Experience

The following adverse reactions have been identified during post approval use of finasteride monotherapy and tadalafil. Because these reactions are reported voluntarily from a population of uncertain size, it is not always possible to reliably estimate their frequency or establish a causal relationship to drug exposure.

Finasteride monotherapy:

- hypersensitivity reactions, such as pruritus, urticaria, and angioedema (including swelling of the lips, tongue, throat, and face)
- testicular pain
- hematospermia
- sexual dysfunction that continued after discontinuation of treatment, including erectile dysfunction, decreased libido and ejaculation disorders (e.g. reduced ejaculate volume)
- male infertility and/or poor seminal quality
- depression
- male breast cancer

Tadalafil:

- Cardiovascular and Cerebrovascular — Serious cardiovascular events, including myocardial infarction, sudden cardiac death, stroke, chest pain, palpitations, and tachycardia
- Body as a Whole — hypersensitivity reactions including urticaria, Stevens-Johnson syndrome, and exfoliative dermatitis
- Nervous — migraine, seizure and seizure recurrence, transient global amnesia
- Ophthalmologic — visual field defect, retinal vein occlusion, retinal artery occlusion Non-arteritic anterior ischemic optic neuropathy (NAION)
- Otologic — Sudden decrease or loss of hearing
- Urogenital — priapism

7 DRUG INTERACTIONS

7.1 Effects of Other Drugs on ENTADFI

CYP3A4 (e.g., Ketoconazole) — Concomitant use of strong inhibitors (e.g., ketoconazole) of CYP3A4 is not recommended as they may increase tadalafil exposure.

7.2 Effects of ENTADFI on Other Drugs

Nitrates — Administration of ENTADFI to patients who are using any form of organic nitrate, is contraindicated. In clinical pharmacology studies, tadalafil was shown to potentiate the hypotensive effect of nitrates. In a patient who has taken ENTADFI, where nitrate administration is deemed medically necessary in a life-threatening situation, at least 48 hours should elapse after the last dose of ENTADFI before nitrate administration is considered. In such circumstances, nitrates should still only be administered under close medical supervision with appropriate hemodynamic monitoring [see Contraindications (4), and Clinical Pharmacology (12.2)].

Guanylate Cyclase Stimulators — Administration of ENTADFI to patients taking a guanylate cyclase (GC) stimulator is contraindicated. ENTADFI may potentiate the hypotensive effects of GC stimulators [see Contraindications (4)].

Alpha-Blockers — Caution is advised when PDE5 inhibitors are coadministered with alpha-blockers. PDE5 inhibitors, including ENTADFI, and alpha-adrenergic blocking agents are both vasodilators with blood-pressure-lowering effects. When vasodilators are used in combination, an additive effect on blood pressure may be anticipated [see Warnings and Precautions (5.3), and Clinical Pharmacology (12.2)].

Antihypertensives — PDE5 inhibitors, including tadalafil, are mild systemic vasodilators. Clinical pharmacology studies were conducted to assess the effect of tadalafil on the potentiation of the blood-pressure-lowering effects of selected antihypertensive medications (amlodipine, angiotensin II receptor blockers, bendrofluazide, enalapril, and metoprolol). Small reductions in blood pressure occurred following coadministration of tadalafil with these agents compared with placebo [see Warnings and Precautions (5.3) and Clinical Pharmacology (12.2)].

7.3 Alcohol

Both alcohol and tadalafil, a PDE5 inhibitor, act as mild vasodilators. When mild vasodilators are taken in combination, blood-pressure-lowering effects of each individual compound may be increased. Substantial consumption of alcohol (e.g., 5 units or greater) in combination with ENTADFI can increase the potential for orthostatic signs and symptoms, including increase in heart rate, decrease in standing blood pressure, dizziness, and headache. Tadalafil did not affect alcohol plasma concentrations and alcohol did not affect tadalafil plasma concentrations [see Warnings and Precautions (5.12) and Clinical Pharmacology (12.2)].

8 USE IN SPECIFIC POPULATIONS

8.1 Pregnancy

Risk Summary

ENTADFI is contraindicated in pregnancy and not indicated for use in females [see Contraindications (4)]. Based on animal studies and its mechanism of action, finasteride, a component of ENTADFI, may cause abnormal development of external genitalia in a male fetus if administered to a pregnant female [see Clinical Pharmacology (12.1)]. In animal reproduction studies, oral administration of finasteride to pregnant rats during the period of major organogenesis resulted in a dose-dependent increase in hypospadias that occurred in 3.6 to 100% of male offspring at maternal doses approximately 0.1 to 86 times the maximum recommended human dose (MRHD) of 5 mg/day; decreased prostatic and seminal vesicular weights, delayed preputial separation and transient nipple development in male offspring at maternal doses approximately 0.03 times the MRHD and decreased anogenital distance in male offspring at maternal doses approximately 0.003 times the MRHD (see Data). Finasteride is a Type II 5α-reductase inhibitor that prevents conversion of testosterone to 5α-dihydrotestosterone (DHT), a hormone necessary for normal development of male genitalia. Abnormal male genital development is an expected consequence when conversion of testosterone to 5α-dihydrotestosterone (DHT) is inhibited by 5α-reductase inhibitors. These outcomes are similar to those reported in male infants with genetic 5α-reductase deficiency.

In animal reproduction studies, no adverse developmental effects were observed with oral administration of tadalafil to pregnant rats or mice during organogenesis at exposures up to 44 times the maximum recommended human dose (MRHD) of 5 mg/day (See Data).

Females of reproductive potential, including pregnant females, should not handle crushed or open ENTADFI capsules because of possible exposure of a male fetus [see Warnings and Precautions (5.7)].

Data

Animal Data

Finasteride:

In an embryo-fetal development study, pregnant rats received finasteride during the period of major organogenesis (gestation days 6 to 17). At maternal doses of oral finasteride approximately 0.1 to 86 times the maximum recommended human dose (MRHD) of 5 mg/day (based on AUC at animal doses of 0.1 to 100 mg/kg/day) there was a dose-dependent increase in hypospadias that occurred in 3.6 to 100% of male offspring. Exposure multiples were estimated using data from nonpregnant rats. Days 16 to 17 of gestation is a critical period in male fetal rats for differentiation of the external genitalia. At oral maternal doses approximately 0.03 times the MRHD (based on AUC at animal dose of 0.03 mg/kg/day), male offspring had decreased prostatic and seminal vesicular weights, delayed preputial separation and transient nipple development. Decreased anogenital distance occurred in male offspring of pregnant rats that received approximately 0.003 times the MRHD (based on AUC at animal dose of 0.003 mg/kg/day). No abnormalities were observed in female offspring at any maternal dose of finasteride.

Slightly decreased fertility was observed in male offspring after administration of about 3 times the MRHD (based on AUC at animal dose of 3 mg/kg/day) to female rats during late gestation and lactation. No effects on fertility were seen in female offspring under these conditions.

No evidence of male external genital malformations or other abnormalities were observed in rabbit fetuses exposed to finasteride during the period of major organogenesis (gestation days 6-18) at maternal oral doses up to 100 mg/kg/day, (finasteride exposure levels were not measured in rabbits). However, this study may not have included the critical period for finasteride effects on development of male external genitalia in the rabbit.

The fetal effects of maternal finasteride exposure were evaluated during the period of embryonic and fetal development from gestation day 20-100 in the rhesus monkey. Intravenous administration of finasteride to pregnant monkeys at doses as high as 800 ng/day (estimated maximal blood concentration of 1.86 ng/mL or about 143 times the highest estimated exposure of pregnant women to finasteride from semen of men taking 5 mg/day) resulted in no abnormalities in male fetuses. However, oral administration of finasteride (2 mg/kg/day or approximately 18,000 times the highest estimated blood levels of finasteride from semen of men taking 5 mg/day) to pregnant monkeys resulted in external genital abnormalities in male fetuses. No other abnormalities were observed in male fetuses and no finasteride-related abnormalities were observed in female fetuses at any dose.

Tadalafil:

Animal reproduction studies showed no evidence of teratogenicity, embryotoxicity, or fetotoxicity when tadalafil was given orally to pregnant rats or mice at exposures up to 44 times the indicated dose of 5 mg/day during organogenesis. In a prenatal/postnatal developmental study in rats, postnatal pup survival decreased following maternal exposure to tadalafil doses greater than 40 times the indicated dose based on AUC. Signs of maternal toxicity occurred at doses greater than 64 times the indicated dose based on AUC. Surviving offspring had normal development and reproductive performance.

In another rat prenatal and postnatal development study at doses of 60, 200, and 1000 mg/kg, a reduction in postnatal survival of pups was observed. The no observed effect level (NOEL) for maternal toxicity was 200 mg/kg/day and for developmental toxicity was 30 mg/kg/day. This gives approximately 64- and 40 fold exposure multiples, respectively, of the human AUC for the indicated dose of 5 mg.

Tadalafil and/or its metabolites cross the placenta, resulting in fetal exposure in rats.

8.2 Lactation

Risk Summary

ENTADFI is not indicated for use in females.

8.3 Females and Males of Reproductive Potential

Infertility

Males

Tadalafil:

There have been no studies evaluating the effect of ENTADFI, including tadalafil, on fertility in men [see Clinical Pharmacology (12.2)].

Based on studies in animals, a decrease in spermatogenesis was observed in dogs, but not in rats [see Nonclinical Toxicology (13.1)].

Fertility Effects

Finasteride:

Treatment with finasteride for 24 weeks to evaluate semen parameters in healthy male volunteers revealed no clinically meaningful effects on sperm concentration, mobility, morphology, or pH. A 0.6 mL (22.1%) median decrease in ejaculate volume with a concomitant reduction in total sperm per ejaculate was observed. These parameters remained within the normal range and were reversible upon discontinuation of therapy with an average time to return to baseline of 84 weeks.

Tadalafil:

Based on the data from 3 studies in adult males, tadalafil decreased sperm concentrations in the study of 10 mg tadalafil for 6 months and the study of 20 mg tadalafil for 9 months. This effect was not seen in the study of 20 mg tadalafil taken for 6 months. There was no adverse effect of tadalafil 10 mg or 20 mg on mean concentrations of testosterone, luteinizing hormone or follicle stimulating hormone. The clinical significance of the decreased sperm concentrations in the two studies is unknown.

8.4 Pediatric Use

The safety and effectiveness of ENTADFI have not been established in patients less than 18 years of age.

8.5 Geriatric Use

ENTADFI is a combination of finasteride and tadalafil.

Finasteride:

Of the total number of finasteride-treated patients in clinical studies for BPH, 1480 and 105 patients were 65 and over and 75 and over, respectively. No overall differences in safety or effectiveness of finasteride have been observed between patients 65 years of age and older and younger adult patients [see Clinical Pharmacology 12.3].

Tadalafil:

Of the total number of tadalafil-treated patients in clinical studies which included an indication for which ENTADFI is not approved, approximately 40 percent were over 65 years of age, while approximately 10 percent were 75 years of age and over. No overall differences in safety or effectiveness of tadalafil have been observed between patients over 65 years of age and younger adult patients. However, in placebo-controlled studies with tadalafil for use as needed for a use for which ENTADFI is not approved, diarrhea was reported more frequently in patients 65 years of age and older who were treated with tadalafil (2.5% of patients). A greater sensitivity in some older individuals should be considered [see Clinical Pharmacology (12.3)].

8.6 Hepatic Impairment

The effect of hepatic impairment on finasteride pharmacokinetics has not been studied. However, finasteride is extensively metabolized in the liver. Exercise caution in the administration of ENTADFI in those patients with mild to moderate hepatic impairment (Child Pugh Class A or B). Insufficient tadalafil data are available for patients with severe hepatic impairment (Child Pugh Class C). Therefore, ENTADFI use is not recommended in these patients. [see Clinical Pharmacology (12.3)].

8.7 Renal Impairment

Due to increased tadalafil exposure (AUC), limited clinical experience, and the lack of ability to influence clearance by dialysis, ENTADFI use is not recommended in patients with creatinine clearance less than 50 mL/min or on hemodialysis [see Clinical Pharmacology (12.3)].

10 OVERDOSAGE

In cases of overdose, standard supportive measures should be adopted as required. Hemodialysis contributes negligibly to tadalafil elimination.

11 DESCRIPTION

ENTADFI (finasteride and tadalafil) capsules are a combination of finasteride and tadalafil for oral administration.

Finasteride:

Finasteride, a synthetic 4-azasteroid compound, is a specific inhibitor of steroid Type II 5α-reductase, an intracellular enzyme that converts the androgen testosterone into 5α-dihydrotestosterone (DHT).

The chemical designation of finasteride is 4-azaandrost-1-ene-17-carboxamide, N-(1,1-dimethylethyl)-3-oxo-,(5α,17β)-. The empirical formula of finasteride is C23H36N2O2 and its molecular weight is 372.55. Its structural formula is:

Finasteride is a white crystalline powder with a melting point near 250°C. It is freely soluble in chloroform and in lower alcohol solvents but is practically insoluble in water.

Tadalafil:

Tadalafil is a selective inhibitor of cyclic guanosine monophosphate (cGMP)-specific phosphodiesterase type 5 (PDE5). Tadalafil has the empirical formula C22H19N3O4 representing a molecular weight of 389.41. The structural formula is:

The chemical designation of tadalafil is pyrazino[1′,2′:1,6]pyrido[3,4-b]indole-1,4-dione, 6-(1,3-benzodioxol-5-yl)2,3,6,7,12,12a-hexahydro-2-methyl-, (6R,12aR)-. It is a crystalline solid that is practically insoluble in water and very slightly soluble in ethanol.

ENTADFI is available as size 3, white opaque capsules for oral administration. Each ENTADFI capsule contains finasteride 5 mg and tadalafil 5 mg and the following inactive ingredients: colloidal silicon dioxide, lactose monohydrate, magnesium stearate, silicified microcrystalline cellulose, sodium lauryl sulfate, and sodium starch glycolate. The capsule shell is composed of carrageenan, hypromellose, potassium chloride, titanium dioxide, and is printed with an edible black printing ink.

12 CLINICAL PHARMACOLOGY

12.1 Mechanism of Action

ENTADFI is a combination of finasteride and tadalafil.

Finasteride:

The development and enlargement of the prostate gland is dependent on the potent androgen, 5α-dihydrotestosterone (DHT). Type II 5α-reductase metabolizes testosterone to DHT in the prostate gland, liver and skin. DHT induces androgenic effects by binding to androgen receptors in the cell nuclei of these organs.

Finasteride is a competitive and specific inhibitor of Type II 5α-reductase with which it slowly forms a stable enzyme complex. Turnover from this complex is extremely slow (t½ ~ 30 days). This has been demonstrated both in vivo and in vitro. Finasteride has no affinity for the androgen receptor. In man, the 5α-reduced steroid metabolites in blood and urine are decreased after administration of finasteride.

Tadalafil:

The mechanism for reducing BPH symptoms has not been established. Studies in vitro have demonstrated that tadalafil is a selective inhibitor of phosphodiesterase 5 (PDE5). PDE5 is found in the smooth muscle of the corpus cavernosum, prostate, and bladder as well as in vascular and visceral smooth muscle, skeletal muscle, urethra, platelets, kidney, lung, cerebellum, heart, liver, testis, seminal vesicle, and pancreas.

In vitro studies have shown that the effect of tadalafil is more potent on PDE5 than on other phosphodiesterases. These studies have shown that tadalafil is >10,000-fold more potent for PDE5 than for PDE1, PDE2, PDE4, and PDE7 enzymes, which are found in the heart, brain, blood vessels, liver, leukocytes, skeletal muscle, and other organs. Tadalafil is >10,000-fold more potent for PDE5 than for PDE3, an enzyme found in the heart and blood vessels. Additionally, tadalafil is 700-fold more potent for PDE5 than for PDE6, which is found in the retina and is responsible for phototransduction. Tadalafil is >9,000-fold more potent for PDE5 than for PDE8, PDE9, and PDE10. Tadalafil is 14-fold more potent for PDE5 than for PDE11A1 and 40-fold more potent for PDE5 than for PDE11A4, two of the four known forms of PDE11. PDE11 is an enzyme found in human prostate, testes, skeletal muscle and in other tissues (e.g., adrenal cortex). In vitro, tadalafil inhibits human recombinant PDE11A1 and, to a lesser degree, PDE11A4 activities at concentrations within the therapeutic range. The physiological role and clinical consequence of PDE11 inhibition in humans have not been defined.

12.2 Pharmacodynamics

Finasteride:

In man, a single 5-mg oral dose of finasteride produces a rapid reduction in serum DHT concentration, with the maximum effect observed 8 hours after the first dose. The suppression of DHT is maintained throughout the 24-hour dosing interval and with continued treatment. Daily dosing of finasteride at 5 mg/day for up to 4 years has been shown to reduce the serum DHT concentration by approximately 70%. The median circulating level of testosterone increased by approximately 10-20% but remained within the physiologic range. In a separate study in healthy men treated with finasteride 1 mg per day (n=82) or placebo (n=69), mean circulating levels of testosterone and estradiol were increased by approximately 15% as compared to baseline, but these remained within the physiologic range.

In patients receiving finasteride 5 mg/day, increases of about 10% were observed in luteinizing hormone (LH) and follicle-stimulating hormone (FSH), but levels remained within the normal range. In healthy volunteers, treatment with finasteride did not alter the response of LH and FSH to gonadotropin-releasing hormone indicating that the hypothalamic-pituitary-testicular axis was not affected.

In patients with BPH, finasteride has no effect on circulating levels of cortisol, prolactin, thyroid-stimulating hormone, or thyroxine. No clinically meaningful effect was observed on the plasma lipid profile (i.e., total cholesterol, low density lipoproteins, high density lipoproteins and triglycerides) or bone mineral density.

Adult males with genetically inherited Type II 5α-reductase deficiency also have decreased levels of DHT. Except for the associated urogenital defects present at birth, no other clinical abnormalities related to Type II 5α-reductase deficiency have been observed in these individuals. These individuals have a small prostate gland throughout life and do not develop BPH.

In patients with BPH treated with finasteride (1-100 mg/day) for 7-10 days prior to prostatectomy, an approximate 80% lower DHT content was measured in prostatic tissue removed at surgery, compared to placebo; testosterone tissue concentration was increased up to 10 times over pretreatment levels, relative to placebo. Intraprostatic content of PSA was also decreased.

In healthy male volunteers treated with finasteride 5 mg/day for 14 days, discontinuation of therapy resulted in a return of DHT levels to pretreatment levels in approximately 2 weeks. In patients treated for three months, prostate volume, which declined by approximately 20%, returned to close to baseline value after approximately three months of discontinuation of therapy.

Tadalafil:

Effects on Blood Pressure

Tadalafil 20 mg administered to healthy male subjects produced no significant difference compared to placebo in supine systolic and diastolic blood pressure (difference in the mean maximal decrease of 1.6/0.8 mm Hg, respectively) and in standing systolic and diastolic blood pressure (difference in the mean maximal decrease of 0.2/4.6 mm Hg, respectively). In addition, there was no significant effect on heart rate.

Effects on Blood Pressure When Administered with Nitrates

In clinical pharmacology studies, tadalafil (5 to 20 mg) was shown to potentiate the hypotensive effect of nitrates. Therefore, the use of ENTADFI in patients taking any form of nitrates is contraindicated [see Contraindications (4)].

A study was conducted to assess the degree of interaction between nitroglycerin and tadalafil, should nitroglycerin be required in an emergency situation after tadalafil was taken. This was a double-blind, placebo-controlled, crossover study in 150 male subjects at least 40 years of age (including subjects with diabetes mellitus and/or controlled hypertension) and receiving daily doses of tadalafil 20 mg or matching placebo for 7 days. Subjects were administered a single dose of 0.4 mg sublingual nitroglycerin (NTG) at pre-specified timepoints, following their last dose of tadalafil (2, 4, 8, 24, 48, 72, and 96 hours after tadalafil). The objective of the study was to determine when, after tadalafil dosing, no apparent blood pressure interaction was observed. In this study, a significant interaction between tadalafil and NTG was observed at each timepoint up to and including 24 hours. At 48 hours, by most hemodynamic measures, the interaction between tadalafil and NTG was not observed, although a few more tadalafil subjects compared to placebo experienced greater blood-pressure lowering at this timepoint. After 48 hours, the interaction was not detectable (see Figure 1).

Figure 1: Mean Maximal Change in Blood Pressure (Tadalafil Minus Placebo, Point Estimate with 90% CI) in Response to Sublingual Nitroglycerin at 2 (Supine Only), 4, 8, 24, 48, 72, and 96 Hours after the Last Dose of Tadalafil 20 mg or Placebo

Therefore, ENTADFI administration with nitrates is contraindicated. In a patient who has taken ENTADFI, where nitrate administration is deemed medically necessary in a life-threatening situation, at least 48 hours should elapse after the last dose of ENTADFI before nitrate administration is considered. In such circumstances, nitrates should still only be administered under close medical supervision with appropriate hemodynamic monitoring [see Contraindications (4)].

Effect on Blood Pressure When Administered With Alpha-Blockers

Six randomized, double-blinded, crossover clinical pharmacology studies were conducted to investigate the potential interaction of tadalafil with alpha-blocker agents in healthy male subjects [see Warnings and Precautions (5.3)]. In four studies, a single oral dose of tadalafil was administered to healthy male subjects taking daily (at least 7 days duration) an oral alpha-blocker. In two studies, a daily oral alpha-blocker (at least 7 days duration) was administered to healthy male subjects taking repeated daily doses of tadalafil.

Doxazosin — Three clinical pharmacology studies were conducted with tadalafil and doxazosin, an alpha[1]-adrenergic blocker.

In the first doxazosin study, a single oral dose of tadalafil 20 mg or placebo was administered in a 2-period, crossover design to healthy subjects taking oral doxazosin 8 mg daily (N=18 subjects). Doxazosin was administered at the same time as tadalafil or placebo after a minimum of seven days of doxazosin dosing (see Table 4 and Figure 2).

Table 4: Doxazosin (8 mg/day) Study 1: Mean Maximal Decrease (95% CI) in Systolic Blood Pressure
Placebo-subtracted mean maximal decrease in systolic blood pressure (mm Hg) | Tadalafil 20 mg
Supine | 3.6 (-1.5, 8.8)
Standing | 9.8 (4.1, 15.5)

Figure 2: Doxazosin Study 1: Mean Change from Baseline in Systolic Blood Pressure

Blood pressure was measured manually at 1, 2, 3, 4, 5, 6, 7, 8, 10, 12, and 24 hours after tadalafil or placebo administration. Outliers were defined as subjects with a standing systolic blood pressure of <85 mm Hg or a decrease from baseline in standing systolic blood pressure of >30 mm Hg at one or more time points. There were nine and three outliers following administration of tadalafil 20 mg and placebo, respectively. Five and two subjects were outliers due to a decrease from baseline in standing systolic BP of >30 mm Hg, while five and one subject were outliers due to standing systolic BP <85 mm Hg following tadalafil and placebo, respectively. Severe adverse events potentially related to blood-pressure effects were assessed. No such events were reported following placebo. Two such events were reported following administration of tadalafil. Vertigo was reported in one subject that began 7 hours after dosing and lasted about 5 days. This subject previously experienced a mild episode of vertigo on doxazosin and placebo. Dizziness was reported in another subject that began 25 minutes after dosing and lasted 1 day. No syncope was reported.

In the second doxazosin study, a single oral dose of tadalafil 20 mg was administered to healthy subjects taking oral doxazosin, either 4 or 8 mg daily. The study (N=72 subjects) was conducted in three parts, each a 3-period crossover.

In part A (N=24), subjects were titrated to doxazosin 4 mg administered daily at 8 a.m. Tadalafil was administered at either 8 a.m., 4 p.m., or 8 p.m. There was no placebo control.

In part B (N=24), subjects were titrated to doxazosin 4 mg administered daily at 8 p.m. Tadalafil was administered at either 8 a.m., 4 p.m., or 8 p.m. There was no placebo control.

In part C (N=24), subjects were titrated to doxazosin 8 mg administered daily at 8 a.m. In this part, tadalafil or placebo were administered at either 8 a.m. or 8 p.m.

The placebo-subtracted mean maximal decreases in systolic blood pressure over a 12-hour period after dosing in the placebo-controlled portion of the study (part C) are shown in Table 5 and Figure 3.

Table 5: Doxazosin (8 mg/day) Study 2 (Part C): Mean Maximal Decrease in Systolic Blood Pressure
Placebo-subtracted mean maximal decrease in systolic blood pressure (mm Hg) | Tadalafil 20 mg at 8 a.m. | Tadalafil 20 mg at 8 p.m.
Ambulatory Blood-Pressure Monitoring (ABPM) | 7 | 8

Figure 3: Doxazosin Study 2 (Part C): Mean Change from Time-Matched Baseline in Systolic Blood Pressure

Blood pressure was measured by ABPM every 15 to 30 minutes for up to 36 hours after tadalafil or placebo. Subjects were categorized as outliers if one or more systolic blood pressure readings of <85 mm Hg were recorded or one or more decreases in systolic blood pressure of >30 mm Hg from a time-matched baseline occurred during the analysis interval.

Of the 24 subjects in part C, 16 subjects were categorized as outliers following administration of tadalafil and 6 subjects were categorized as outliers following placebo during the 24-hour period after 8 a.m. dosing of tadalafil or placebo. Of these, 5 and 2 were outliers due to systolic BP <85 mm Hg, while 15 and 4 were outliers due to a decrease from baseline in systolic BP of >30 mm Hg following tadalafil and placebo, respectively.

During the 24-hour period after 8 p.m. dosing, 17 subjects were categorized as outliers following administration of tadalafil and 7 subjects following placebo. Of these, 10 and 2 subjects were outliers due to systolic BP <85 mm Hg, while 15 and 5 subjects were outliers due to a decrease from baseline in systolic BP of >30 mm Hg, following tadalafil and placebo, respectively.

Some additional subjects in both the tadalafil and placebo groups were categorized as outliers in the period beyond 24 hours.

Severe adverse events potentially related to blood-pressure effects were assessed. In the study (N=72 subjects), 2 such events were reported following administration of tadalafil (symptomatic hypotension in one subject that began 10 hours after dosing and lasted approximately 1 hour, and dizziness in another subject that began 11 hours after dosing and lasted 2 minutes). No such events were reported following placebo. In the period prior to tadalafil dosing, one severe event (dizziness) was reported in a subject during the doxazosin run-in phase.

In the third doxazosin study, healthy subjects (N=45 treated; 37 completed) received 28 days of once per day dosing of tadalafil 5 mg or placebo in a two-period crossover design. After 7 days, doxazosin was initiated at 1 mg and titrated up to 4 mg daily over the last 21 days of each period (7 days on 1 mg; 7 days of 2 mg; 7 days of 4 mg doxazosin). The results are shown in Table 6.

Table 6: Doxazosin Study 3: Mean Maximal Decrease (95% CI) in Systolic Blood Pressure
Placebo-subtracted mean maximal decrease in systolic blood pressure |  | Tadalafil 5 mg
Day 1 of 4 mg Doxazosin | Supine | 2.4 (-0.4, 5.2)
 | Standing | -0.5 (-4.0, 3.1)
Day 7 of 4 mg Doxazosin | Supine | 2.8 (-0.1, 5.7)
 | Standing | 1.1 (-2.9, 5.0)

Blood pressure was measured manually pre-dose at two time points (-30 and -15 minutes) and then at 1, 2, 3, 4, 5, 6, 7, 8, 10, 12 and 24 hours post dose on the first day of each doxazosin dose, (1 mg, 2 mg, 4 mg), as well as on the seventh day of 4 mg doxazosin administration.

Following the first dose of doxazosin 1 mg, there were no outliers on tadalafil 5 mg and one outlier on placebo due to a decrease from baseline in standing systolic BP of >30 mm Hg.

There were 2 outliers on tadalafil 5 mg and none on placebo following the first dose of doxazosin 2 mg due to a decrease from baseline in standing systolic BP of >30 mm Hg.

There were no outliers on tadalafil 5 mg and two on placebo following the first dose of doxazosin 4 mg due to a decrease from baseline in standing systolic BP of >30 mm Hg. There was one outlier on tadalafil 5 mg and three on placebo following the first dose of doxazosin 4 mg due to standing systolic BP <85 mm Hg. Following the seventh day of doxazosin 4 mg, there were no outliers on tadalafil 5 mg, one subject on placebo had a decrease >30 mm Hg in standing systolic blood pressure, and one subject on placebo had standing systolic blood pressure <85 mm Hg. All adverse events potentially related to blood pressure effects were rated as mild or moderate. There were two episodes of syncope in this study, one subject following a dose of tadalafil 5 mg alone, and another subject following coadministration of tadalafil 5 mg and doxazosin 4 mg.

Tamsulosin — In the first tamsulosin study, a single oral dose of tadalafil 10, 20 mg, or placebo was administered in a 3 period, crossover design to healthy subjects taking 0.4 mg once per day tamsulosin, a selective alpha[1A]-adrenergic blocker (N=18 subjects). Tadalafil or placebo was administered 2 hours after tamsulosin following a minimum of seven days of tamsulosin dosing.

Table 7: Tamsulosin (0.4 mg/day) Study 1: Mean Maximal Decrease (95% CI) in Systolic Blood Pressure
Placebo-subtracted mean maximal decrease in systolic blood pressure (mm Hg) | Tadalafil 10 mg | Tadalafil 20 mg
Supine | 3.2 (-2.3, 8.6) | 3.2 (-2.3, 8.7)
Standing | 1.7 (-4.7, 8.1) | 2.3 (-4.1, 8.7)

Blood pressure was measured manually at 1, 2, 3, 4, 5, 6, 7, 8, 10, 12, and 24 hours after tadalafil or placebo dosing. There were 2, 2, and 1 outliers (subjects with a decrease from baseline in standing systolic blood pressure of >30 mm Hg at one or more time points) following administration of tadalafil 10 mg, 20 mg, and placebo, respectively. There were no subjects with a standing systolic blood pressure <85 mm Hg. No severe adverse events potentially related to blood-pressure effects were reported. No syncope was reported.

In the second tamsulosin study, healthy subjects (N=39 treated; and 35 completed) received 14 days of once per day dosing of tadalafil 5 mg or placebo in a two-period crossover design. Daily dosing of tamsulosin 0.4 mg was added for the last seven days of each period.

Table 8: Tamsulosin Study 2: Mean Maximal Decrease (95% CI) in Systolic Blood Pressure
Placebo-subtracted mean maximal decrease in systolic blood pressure |  | Tadalafil 5 mg
Day 1 of 0.4 mg Tamsulosin | Supine | -0.1 (-2.2, 1.9)
 | Standing | 0.9 (-1.4, 3.2)
Day 7 of 0.4 mg Tamsulosin | Supine | 1.2 (-1.2, 3.6)
 | Standing | 1.2 (-1.0, 3.5)

Blood pressure was measured manually pre-dose at two time points (-30 and -15 minutes) and then at 1, 2, 3, 4, 5, 6, 7, 8, 10, 12, and 24 hours post dose on the first, sixth and seventh days of tamsulosin administration. There were no outliers (subjects with a decrease from baseline in standing systolic blood pressure of >30 mm Hg at one or more time points). One subject on placebo plus tamsulosin (Day 7) and one subject on tadalafil plus tamsulosin (Day 6) had standing systolic blood pressure <85 mm Hg. No severe adverse events potentially related to blood pressure were reported. No syncope was reported.

Alfuzosin — A single oral dose of tadalafil 20 mg or placebo was administered in a 2-period, crossover design to healthy subjects taking once-daily alfuzosin HCl 10 mg extended-release tablets, an alpha[1]-adrenergic blocker (N=17 completed subjects). Tadalafil or placebo was administered 4 hours after alfuzosin following a minimum of seven days of alfuzosin dosing.

Table 9: Alfuzosin (10 mg/day) Study: Mean Maximal Decrease (95% CI) in Systolic Blood Pressure
Placebo-subtracted mean maximal decrease in systolic blood pressure (mm Hg) | Tadalafil 20 mg
Supine | 2.2 (-0.9,-5.2)
Standing | 4.4 (-0.2, 8.9)

Blood pressure was measured manually at 1, 2, 3, 4, 6, 8, 10, 20, and 24 hours after tadalafil or placebo dosing. There was 1 outlier (subject with a standing systolic blood pressure <85 mm Hg) following administration of tadalafil 20 mg. There were no subjects with a decrease from baseline in standing systolic blood pressure of >30 mm Hg at one or more time points. No severe adverse events potentially related to blood pressure effects were reported. No syncope was reported.

Effects on Blood Pressure When Administered with Antihypertensives

Amlodipine — A study was conducted to assess the interaction of amlodipine (5 mg daily) and tadalafil 10 mg. There was no effect of tadalafil on amlodipine blood levels and no effect of amlodipine on tadalafil blood levels. The mean reduction in supine systolic/diastolic blood pressure due to tadalafil 10 mg in subjects taking amlodipine was 3/2 mm Hg, compared to placebo. In a similar study using tadalafil 20 mg, there were no clinically significant differences between tadalafil and placebo in subjects taking amlodipine.

Angiotensin II receptor blockers (with and without other antihypertensives) — A study was conducted to assess the interaction of angiotensin II receptor blockers and tadalafil 20 mg. Subjects in the study were taking any marketed angiotensin II receptor blocker, either alone, as a component of a combination product, or as part of a multiple antihypertensive regimen. Following dosing, ambulatory measurements of blood pressure revealed differences between tadalafil and placebo of 8/4 mm Hg in systolic/diastolic blood pressure.

Bendrofluazide — A study was conducted to assess the interaction of bendrofluazide (2.5 mg daily) and tadalafil 10 mg. Following dosing, the mean reduction in supine systolic/diastolic blood pressure due to tadalafil 10 mg in subjects taking bendrofluazide was 6/4 mm Hg, compared to placebo.

Enalapril — A study was conducted to assess the interaction of enalapril (10 to 20 mg daily) and tadalafil 10 mg. Following dosing, the mean reduction in supine systolic/diastolic blood pressure due to tadalafil 10 mg in subjects taking enalapril was 4/1 mm Hg, compared to placebo.

Metoprolol — A study was conducted to assess the interaction of sustained-release metoprolol (25 to 200 mg daily) and tadalafil 10 mg. Following dosing, the mean reduction in supine systolic/diastolic blood pressure due to tadalafil 10 mg in subjects taking metoprolol was 5/3 mm Hg, compared to placebo.

Effects on Blood Pressure When Administered with Alcohol

Alcohol and PDE5 inhibitors, including tadalafil, are mild systemic vasodilators. The interaction of tadalafil with alcohol was evaluated in 3 clinical pharmacology studies. In 2 of these, alcohol was administered at a dose of 0.7 g/kg, which is equivalent to approximately 6 ounces of 80-proof vodka in an 80-kg male, and tadalafil was administered at a dose of 10 mg in one study and 20 mg in another. In both these studies, all patients imbibed the entire alcohol dose within 10 minutes of starting. In one of these two studies, blood alcohol levels of 0.08% were confirmed. In these two studies, more patients had clinically significant decreases in blood pressure on the combination of tadalafil and alcohol as compared to alcohol alone. Some subjects reported postural dizziness, and orthostatic hypotension was observed in some subjects. When tadalafil 20 mg was administered with a lower dose of alcohol (0.6 g/kg, which is equivalent to approximately 4 ounces of 80-proof vodka, administered in less than 10 minutes), orthostatic hypotension was not observed, dizziness occurred with similar frequency to alcohol alone, and the hypotensive effects of alcohol were not potentiated.

Tadalafil did not affect alcohol plasma concentrations and alcohol did not affect tadalafil plasma concentrations.

Effects on Exercise Stress Testing

The effects of tadalafil on cardiac function, hemodynamics, and exercise tolerance were investigated in a single clinical pharmacology study. In this blinded crossover trial, 23 subjects with stable coronary artery disease and evidence of exercise-induced cardiac ischemia were enrolled. The primary endpoint was time to cardiac ischemia. The mean difference in total exercise time was 3 seconds (tadalafil 10 mg minus placebo), which represented no clinically meaningful difference. Further statistical analysis demonstrated that tadalafil was non-inferior to placebo with respect to time to ischemia. Of note, in this study, in some subjects who received tadalafil followed by sublingual nitroglycerin in the post-exercise period, clinically significant reductions in blood pressure were observed, consistent with the augmentation by tadalafil of the blood-pressure-lowering effects of nitrates.

Effects on Vision

Single oral doses of phosphodiesterase inhibitors have demonstrated transient dose-related impairment of color discrimination (blue/green), using the Farnsworth-Munsell 100-hue test, with peak effects near the time of peak plasma levels. This finding is consistent with the inhibition of PDE6, which is involved in phototransduction in the retina. In a study to assess the effects of a single dose of tadalafil 40 mg on vision (N=59), no effects were observed on visual acuity, intraocular pressure, or pupilometry. Across all clinical studies with tadalafil, reports of changes in color vision were rare (<0.1% of patients).

Effects on Sperm Characteristics

Three studies were conducted in men to assess the potential effect on sperm characteristics of tadalafil 10 mg (one 6 month study) and 20 mg (one 6 month and one 9 month study) administered daily. There were no adverse effects on sperm morphology or sperm motility in any of the three studies. In the study of 10 mg tadalafil for 6 months and the study of 20 mg tadalafil for 9 months, results showed a decrease in mean sperm concentrations relative to placebo, although these differences were not clinically meaningful. This effect was not seen in the study of 20 mg tadalafil taken for 6 months. In addition there was no adverse effect on mean concentrations of reproductive hormones, testosterone, luteinizing hormone or follicle stimulating hormone with either 10 or 20 mg of tadalafil compared to placebo.

Effects on Cardiac Electrophysiology

The effect of a single 100-mg dose of tadalafil on the QT interval was evaluated at the time of peak tadalafil concentration in a randomized, double-blinded, placebo, and active (intravenous ibutilide) -controlled crossover study in 90 healthy males aged 18 to 53 years. The mean change in QTc (Fridericia QT correction) for tadalafil, relative to placebo, was 3.5 milliseconds (two-sided 90% CI=1.9, 5.1). The mean change in QTc (Individual QT correction) for tadalafil, relative to placebo, was 2.8 milliseconds (two-sided 90% CI=1.2, 4.4). A 100-mg dose of tadalafil (20 times the highest recommended dose) was chosen because this dose yields exposures covering those observed upon coadministration of tadalafil with strong CYP3A4 inhibitors or those observed in renal impairment. In this study, the mean increase in heart rate associated with a 100-mg dose of tadalafil compared to placebo was 3.1 beats per minute.

12.3 Pharmacokinetics

The pharmacokinetic parameter of finasteride and tadalafil after single dose administration of ENTADFI under fasted conditions are summarized in Table 10.

Table 10: Pharmacokinetic Parameters of Finasteride and Tadalafil After Single Dose Administration of ENTADFI
 | Finasteride |  | Tadalafil
 | Mean | CV (%) | Mean | CV (%)
Cmax (ng/mL) | 43.224 | (24.1) | 106.751 | (23.6)
Tmax (hours) [Median and range are presented] | 2.00 | (1.00-4.07) | 3.00 | (1.00-4.05)
AUCt (ng•h/mL) | 335.811 | (28.0) | 2507.502 | (31.9)
AUC0-∞ (ng•h/mL) | 339.832 | (28.5) | 2628.645 | (35.3)
t1/2 | 6.63 | (24.5) | 22.33 | (24.9)
Abbreviations: CV = coefficient of variation

Absorption

Finasteride

In a study of 15 healthy young subjects, the mean bioavailability of finasteride 5 mg tablets was 63% (range 34-108%).

Tadalafil

Absolute bioavailability of tadalafil following oral dosing has not been determined.

Effect of Food

The Cmax of finasteride and tadalafil were decreased by 29% and 23%, respectively, after administration of ENTADFI following consumption of a high-fat, high-calorie meal (i.e., 1011 calorie meal in which 53% of calories are derived from fat) compared with the fasted state. The administration of ENTADFI with high-fat, high-calorie meal did not affect the extent of absorption (AUCt and AUC∞) for finasteride and tadalafil.

Distribution

Finasteride

Mean steady-state volume of distribution was 76 liters (range, 44-96 liters). Approximately 90% of circulating finasteride is bound to plasma proteins.

Finasteride has been shown to cross the blood brain barrier but does not appear to distribute preferentially to the CSF.

In two studies of healthy subjects (n=69) receiving finasteride 5 mg/day for 6-24 weeks, finasteride concentrations in semen ranged from undetectable (<0.1 ng/mL) to 10.54 ng/mL. In an earlier study using a less sensitive assay, finasteride concentrations in the semen of 16 subjects receiving finasteride 5 mg/day ranged from undetectable (<1.0 ng/mL) to 21 ng/mL. Thus, based on a 5-mL ejaculate volume, the amount of finasteride in semen was estimated to be 50- to 100-fold less than the dose of finasteride (5 µg) that had no effect on circulating DHT levels in men [see also Use in Specific Populations (8.3)].

Tadalafil

The mean apparent volume of distribution following oral administration is approximately 63 L, indicating that tadalafil is distributed into tissues. At therapeutic concentrations, 94% of tadalafil in plasma is bound to proteins.

Less than 0.0005% of the administered dose appeared in the semen of healthy subjects.

Elimination

Metabolism

Finasteride

Finasteride is extensively metabolized in the liver, primarily via CYP3A4. Two metabolites, the t-butyl side chain monohydroxylated and monocarboxylic acid metabolites, have been identified that possess no more than 20% of the 5α-reductase inhibitory activity of finasteride.

Tadalafil

Tadalafil is predominantly metabolized by CYP3A4 to a catechol metabolite. The catechol metabolite undergoes extensive methylation and glucuronidation to form the methylcatechol and methylcatechol glucuronide conjugate, respectively. The major circulating metabolite is the methylcatechol glucuronide. Methylcatechol concentrations are less than 10% of glucuronide concentrations. In vitro data suggests that metabolites are not expected to be pharmacologically active at observed metabolite concentrations.

Excretion

Finasteride

Following an oral dose of ^14C-finasteride in man (n=6), a mean of 39% (range, 32-46%) of the dose was excreted in the urine in the form of metabolites; 57% (range, 51-64%) was excreted in the feces.

Tadalafil

Tadalafil is excreted predominantly as metabolites, mainly in the feces (approximately 61% of the dose) and to a lesser extent in the urine (approximately 36% of the dose).

Specific Populations

Geriatric Patients

No dosage adjustment of ENTADFI is necessary in the elderly. In patients with BPH following single and multiple doses of 20 mg tadalafil, no statistically significant differences in exposure (AUC and Cmax) were observed between elderly (70 to 85 years) and younger (≤60 years of age) subjects. Healthy male elderly subjects (65 years or over) had a lower renal clearance of tadalafil, resulting in 25% higher exposure (AUC) with no effect on Cmax relative to that observed in healthy subjects 19 to 45 years of age. No dose adjustment is warranted based on age alone. However, greater sensitivity to medications in some older individuals should be considered [see Use in Specific Populations (8.5)].

Although the elimination rate of finasteride is decreased in the elderly, these findings are of no clinical significance [see Use in Specific Populations (8.5)].

Table 11: Mean (SD) Noncompartmental Pharmacokinetic Parameters After Multiple Doses of 5 mg/day in Older Men
 | Mean (± SD)
 | 45-60 years old (n=12) | 70 years old (n=12)
AUC (ng∙hr/mL) | 389 (98) | 463 (186)
Cmax (ng/mL) | 46.2 (8.7) | 48.4 (14.7)
Tmax (hours) | 1.8 (0.7) | 1.8 (0.6)
t1/2 (hours) [First-dose values; all other parameters are last-dose values] | 6.0 (1.5) | 8.2 (2.5)

Race

The effect of race on the pharmacokinetics of finasteride or tadalafil has not been studied.

Patients with Diabetes Mellitus

In male patients with diabetes mellitus after a 10 mg tadalafil dose, exposure (AUC) was reduced approximately 19% and Cmax was 5% lower than that observed in healthy subjects. The dose of tadalafil in ENTADFI is 5 mg per day. No dose adjustment is warranted with ENTADFI in patients with diabetes mellitus.

Patients with Renal Impairment

Finasteride

In patients with chronic renal impairment, with creatinine clearances ranging from 9.0 to 55 mL/min, AUC, maximum plasma concentration, half-life, and protein binding of finasteride after a single dose of ^14C-finasteride were similar to values obtained in healthy volunteers. Plasma concentrations of metabolites were significantly higher in patients with renal impairment (based on a 60% increase in total radioactivity AUC). The increased plasma concentrations of finasteride metabolites were not clinically meaningful.

Tadalafil

In clinical pharmacology studies using single-dose tadalafil (5 to 10 mg), tadalafil exposure (AUC) doubled in subjects with creatinine clearance 30 to 80 mL/min. In subjects with end-stage renal disease on hemodialysis, there was a 2-fold increase in Cmax and 2.7-to 4.8-fold increase in AUC following single-dose administration of 10 or 20 mg tadalafil. Exposure to total methylcatechol (unconjugated plus glucuronide) was 2-to 4-fold higher in subjects with renal impairment, compared to those with normal renal function. Hemodialysis (performed between 24- and 30-hour post-dose) contributed negligibly to tadalafil or metabolite elimination. In a clinical pharmacology study (N=28) at a dose of 10 mg, back pain was reported as a limiting adverse event in male patients with creatinine clearance 30 to 50 mL/min. At a dose of 5 mg, the incidence and severity of back pain was not significantly different than in the general population. In patients on hemodialysis taking 10-or 20-mg tadalafil, there were no reported cases of back pain [see Use in Specific Populations (8.7)].

Patients with Hepatic Impairment

Finasteride

The effect of hepatic impairment on finasteride pharmacokinetics has not been studied.

Tadalafil

In clinical pharmacology studies, tadalafil exposure (AUC) in patients with mild or moderate hepatic impairment (Child-Pugh Class A or B) was comparable to exposure in healthy subjects when a dose of 10 mg was administered. Insufficient data are available for patients with severe hepatic impairment (Child-Pugh Class C) [see Use in Specific Populations (8.6)].

Drug Interaction Studies

Clinical Studies

Finasteride

No drug interactions of clinical importance have been identified for finasteride. Finasteride does not appear to affect the cytochrome P450-linked drug metabolizing enzyme system. Compounds that have been tested in man have included antipyrine, digoxin, propranolol, theophylline, and warfarin and no clinically meaningful interactions were found.

Although specific interaction studies were not performed, finasteride was concomitantly used in clinical studies with acetaminophen, acetylsalicylic acid, α-blockers, angiotensin-converting enzyme (ACE) inhibitors, analgesics, anti-convulsant, beta-adrenergic blocking agents, diuretics, calcium channel blockers, cardiac nitrates, HMG-CoA reductase inhibitors, nonsteroidal anti-inflammatory drugs (NSAIDs), benzodiazepines, H2 antagonists and quinolone anti-infectives without evidence of clinically significant adverse interactions.

Tadalafil

Antacids — Simultaneous administration of an antacid (magnesium hydroxide/aluminum hydroxide) and tadalafil reduced the apparent rate of absorption of tadalafil without altering exposure (AUC) to tadalafil.

H 2 Antagonists (e.g., Nizatidine) — An increase in gastric pH resulting from administration of nizatidine had no significant effect on pharmacokinetics.

CYP3A4 inhibitors — Ketoconazole (400 mg daily), a selective and strong inhibitor of CYP3A4, increased tadalafil 20 mg single-dose exposure (AUC) by 312% and Cmax by 22%, relative to the values for tadalafil 20 mg alone. Ketoconazole (200 mg daily) increased tadalafil 10-mg single-dose exposure (AUC) by 107% and Cmax by 15%, relative to the values for tadalafil 10 mg alone.

HIV Protease inhibitors — Ritonavir (500 mg or 600 mg twice daily at steady state), an inhibitor of CYP3A4, CYP2C9, CYP2C19, and CYP2D6, increased tadalafil 20-mg single-dose exposure (AUC) by 32% with a 30% reduction in Cmax, relative to the values for tadalafil 20 mg alone. Ritonavir (200 mg twice daily), increased tadalafil 20-mg single-dose exposure (AUC) by 124% with no change in Cmax, relative to the values for tadalafil 20 mg alone.

CYP3A4 inducers — Rifampin (600 mg daily), a CYP3A4 inducer, reduced tadalafil 10-mg single-dose exposure (AUC) by 88% and Cmax by 46%, relative to the values for tadalafil 10 mg alone.

Aspirin — Tadalafil did not potentiate the increase in bleeding time caused by aspirin.

CYP1A2 substrates — Tadalafil had no significant effect on the pharmacokinetics of theophylline (CYP1A2 substrate). When tadalafil was administered to subjects taking theophylline, a small augmentation (3 beats per minute) of the increase in heart rate associated with theophylline was observed.

CYP2C9 substrates — Tadalafil had no significant effect on exposure (AUC) to S-warfarin or R-warfarin (CYP2C9 substrate), nor did tadalafil affect changes in prothrombin time induced by warfarin.

CYP3A4 substrates — Tadalafil had no significant effect on exposure (AUC) to midazolam or lovastatin (CYP3A4 substrates).

P-glycoprotein (P-gp) substrates — Coadministration of tadalafil (40 mg once per day) for 10 days did not have a significant effect on the steady-state pharmacokinetics of digoxin (P-gp substrate) administered 0.25 mg/day in healthy subjects.

In Vitro Studies

Tadalafil does not inhibit or induce CYP1A2, CYP3A4, CYP2C9, CYP2C19, CYP2D6, and CYP2E1.

13 NONCLINICAL TOXICOLOGY

13.1 Carcinogenesis, Mutagenesis, Impairment of Fertility

Carcinogenesis —

Finasteride: No evidence of a tumorigenic effect was observed in a 24-month study in Sprague-Dawley rats receiving doses of finasteride up to 160 mg/kg/day in males and 320 mg/kg/day in females. These doses produced respective systemic exposure in rats of 111 and 274 times those observed in man receiving the recommended human dose of 5 mg/day. All exposure calculations were based on calculated AUC(0-24 hr) for animals and mean AUC(0-24 hr) for man (0.4 μg•hr/mL). In a 19-month carcinogenicity study in CD-1 mice, a statistically significant (p≤0.05) increase in the incidence of testicular Leydig cell adenomas was observed at 228 times the human exposure (250 mg/kg/day). In mice at 23 times the human exposure (25 mg/kg/day) and in rats at 39 times the human exposure (40 mg/kg/day) an increase in the incidence of Leydig cell hyperplasia was observed. A positive correlation between the proliferative changes in the Leydig cells and an increase in serum LH levels (2- to 3-fold above control) has been demonstrated in both rodent species treated with high doses of finasteride. No drug-related Leydig cell changes were seen in either rats or dogs treated with finasteride for 1 year at 30 and 350 times (20 mg/kg/day and 45 mg/kg/day, respectively) or in mice treated for 19 months at 2.3 times the human exposure, estimated (2.5 mg/kg/day).

Tadalafil: Tadalafil was not carcinogenic to rats or mice when administered daily for 2 years at doses up to 400 mg/kg/day. Systemic drug exposures, as measured by AUC of unbound tadalafil, were approximately 40-fold for mice, and 56-and 104-fold for male and female rats, respectively, the exposures in human males given the indicated dose of 5 mg.

Mutagenesis —

Finasteride: No evidence of mutagenicity was observed in an in vitro bacterial mutagenesis assay, a mammalian cell mutagenesis assay, or in an in vitro alkaline elution assay. In an in vitro chromosome aberration assay, using Chinese hamster ovary cells, there was a slight increase in chromosome aberrations. These concentrations correspond to 4000-5000 times the peak plasma levels in man given a total dose of 5 mg. In an in vivo chromosome aberration assay in mice, no treatment-related increase in chromosome aberration was observed with finasteride at the maximum tolerated dose of 250 mg/kg/day (228 times the human exposure) as determined in the carcinogenicity studies.

Tadalafil: Tadalafil was not mutagenic in the in vitro bacterial Ames assays or the forward mutation test in mouse lymphoma cells. Tadalafil was not clastogenic in the in vitro chromosomal aberration test in human lymphocytes or the in vivo rat micronucleus assays.

Impairment of Fertility —

Finasteride: In sexually mature male rabbits treated with finasteride at 543 times the human exposure (80 mg/kg/day) for up to 12 weeks, no effect on fertility, sperm count, or ejaculate volume was seen. In sexually mature male rats treated with 61 times the human exposure (80 mg/kg/day), there were no significant effects on fertility after 6 or 12 weeks of treatment; however, when treatment was continued for up to 24 or 30 weeks, there was an apparent decrease in fertility, fecundity and an associated significant decrease in the weights of the seminal vesicles and prostate. All these effects were reversible within 6 weeks of discontinuation of treatment. No drug-related effect on testes or on mating performance has been seen in rats or rabbits. This decrease in fertility in finasteride-treated rats is secondary to its effect on accessory sex organs (prostate and seminal vesicles) resulting in failure to form a seminal plug. The seminal plug is essential for normal fertility in rats and is not relevant in man.

Tadalafil: There were no effects on fertility, reproductive performance or reproductive organ morphology in male or female rats given oral doses of tadalafil up to 400 mg/kg/day, a dose producing AUCs for unbound tadalafil of 56-fold for males or 104-fold for females the exposures observed in human males given the indicated dose of 5 mg. In beagle dogs given tadalafil daily for 3 to 12 months, there was treatment-related non-reversible degeneration and atrophy of the seminiferous tubular epithelium in the testes in 20-100% of the dogs that resulted in a decrease in spermatogenesis in 40-75% of the dogs at doses of ≥10 mg/kg/day. Systemic exposure (based on AUC) at no-observed-adverse-effect level (NOAEL) (10 mg/kg/day) for unbound tadalafil was similar to that expected in humans at a dose of 20 mg. There were no treatment-related testicular findings in rats or mice treated with doses up to 400 mg/kg/day for 2 years.

13.2 Animal Toxicology and/or Pharmacology

Animal studies showed vascular inflammation in tadalafil-treated mice, rats, and dogs. In mice and rats, lymphoid necrosis and hemorrhage were seen in the spleen, thymus, and mesenteric lymph nodes at unbound tadalafil exposure of 8-to 132-fold above the human exposure (AUCs) at the indicated dose of 5 mg. In dogs, an increased incidence of disseminated arteritis was observed in 1-and 6-month studies at unbound tadalafil exposure of 4-to 216-fold above the human exposure (AUC) at the indicated dose of 5 mg. In a 12-month dog study, no disseminated arteritis was observed, but 2 dogs exhibited marked decreases in white blood cells (neutrophils) and moderate decreases in platelets with inflammatory signs at unbound tadalafil exposures of approximately 56-to 72-fold the human exposure at the indicated dose of 5 mg. The abnormal blood-cell findings were reversible within 2 weeks after stopping treatment.

14 CLINICAL STUDIES

The efficacy of ENTADFI is based on an adequate and well-controlled study of tadalafil co-administered with finasteride. Below is the description of this study.

Tadalafil for once daily use initiated together with finasteride was shown to be effective in treating the signs and symptoms of BPH in men with an enlarged prostate (>30 cc) for up to 26 weeks. A double-blinded, parallel-design study of 26 weeks duration randomized 696 men to initiate either tadalafil 5 mg with finasteride 5 mg or placebo with finasteride 5 mg. The study population had a mean age of 64 years (range 46-86). Patients with multiple co-morbid conditions such as erectile dysfunction, diabetes mellitus, hypertension, and other cardiovascular disease were included.

Tadalafil and finasteride administered together demonstrated statistically significant improvement in the signs and symptoms of BPH compared to placebo with finasteride, as measured by the total symptom score (IPSS) at 12 weeks, the primary study endpoint (see Table 12). Key secondary endpoints demonstrated improvement in total IPSS starting at the first scheduled observation at week 4 (tadalafil -4.0, placebo -2.3: p<.001) and the score remained decreased through 26 weeks (tadalafil -5.5, placebo -4.5; p=.022). However, the magnitude of the treatment difference between placebo/finasteride and tadalafil/finasteride decreased from 1.7 points at Week 4 to 1.0 point at Week 26, as shown in Table 12 and in Figure 4. The incremental benefit of ENTADFI beyond 26 weeks is unknown.

Table 12: Mean Total IPSS Changes in BPH Patients in a Tadalafil Study Together with Finasteride
 |  | Placebo and Finasteride 5 mg |  | Tadalafil 5 mg and Finasteride 5 mg | Treatment Difference
 | n | (N=350) [Overall ITT population.] | n | (N=345) |  | p-value [Mixed model for repeated measurements.]
Total Symptom Score (IPSS)
Baseline [Unadjusted mean.] | 349 | 17.4 | 344 | 17.1
Change from Baseline to Week 4 | 340 | -2.3 | 330 | -4.0 | -1.7 | <0.001
Change from Baseline to Week 12 | 318 | -3.8 | 317 | -5.2 | -1.4 | 0.001
Change from Baseline to Week 26 | 295 | -4.5 | 308 | -5.5 | -1.0 | 0.022

Figure 4: Mean Total IPSS Changes By Visit in BPH Patients Taking Tadalafil Together with Finasteride

16 HOW SUPPLIED/STORAGE AND HANDLING

ENTADFI is a combination of finasteride and tadalafil.

How Supplied

ENTADFI capsules contain finasteride 5 mg and tadalafil 5 mg. The size 3 capsules have an opaque white cap and body with a black two-line bar printed on the cap and body.

ENTADFI is supplied as follows: HDPE bottles with a low moisture polyester coil and sealed with a heat-sealed foil HDPE cap as 30-count per bottle (NDC 69681-125-30) or 90-count per bottle (NDC 69681-125-90).

Storage and Handling

Store at 20°C to 25°C (68°F to 77°F); excursions permitted to 15°C to 30°C (59°F to 86°F) [see USP Controlled Room Temperature].

17 PATIENT COUNSELING INFORMATION

See FDA-Approved Patient Labeling (Patient Information).

Cardiovascular Risk

Inform patients that concomitant use of ENTADFI with nitrates could cause blood pressure to suddenly drop to an unsafe level, resulting in dizziness, syncope, or even heart attack or stroke. Advise patients not to take ENTADFI with nitrates unless directly instructed to do so by a health care provider [see Warnings and Precautions (5.1 and 5.3)].

Concomitant Use with Guanylate Cyclase (GC) Stimulators

Advise patients not to take GC stimulators when taking ENTADFI because concomitant use may cause blood pressure to drop to an unsafe level [see Contraindications (4)].

Concomitant Use with Alpha-blockers or Other Antihypertensives

Advise patients of the potential for ENTADFI to augment the blood-pressure-lowering effect of alpha-blockers and antihypertensive medications [see Warnings and Precautions (5.3)].

Increased Risk of High-Grade Prostate Cancer

Inform patients that there was an increase in high-grade prostate cancer in men treated with 5α-reductase inhibitors indicated for BPH treatment, including finasteride, compared to those treated with placebo in studies looking at the use of these drugs to prevent prostate cancer [see Warnings and Precautions (5.5)].

Risks to Male Fetus from Topical Exposure of ENTADFI to Pregnant Females

Inform patients that pregnant females should not handle crushed or open ENTADFI capsules because of the possibility of absorption of finasteride and the subsequent potential risk to the male fetus of a pregnant individual. Advise pregnant females who come in contact with crushed or open ENTADFI capsules to immediately wash the area with soap and water [see Warnings and Precautions (5.7)].

Prolonged Erection and Priapism

Inform patients that ENTADFI may cause prolonged erections greater than 4 hours and priapism (painful erections greater than 6 hours in duration). Advise patients that priapism, if not treated promptly, can result in irreversible damage to the erectile tissue. Advise patients who have an erection lasting greater than 4 hours, whether painful or not, to seek emergency medical attention [see Warnings and Precautions (5.9)].

Ocular Adverse Reactions

Advise patients to stop use of all PDE5 inhibitors, including ENTADFI, and seek medical attention in the event of a sudden loss of vision in one or both eyes. Inform patients that such an event may be a sign of non-arteritic anterior ischemic optic neuropathy (NAION), a cause of decreased vision, including possible permanent loss of vision, that has been reported rarely postmarketing in temporal association with the use of all PDE5 inhibitors [see Warnings and Precautions (5.10)].

Sudden Hearing Loss

Advise patients to stop taking PDE5 inhibitors, including ENTADFI, and seek prompt medical attention in the event of sudden decrease or loss of hearing. Inform patients that these events, which may be accompanied by tinnitus and dizziness, have been reported in temporal association to the intake of PDE5 inhibitors, such as ENTADFI [Warning and Precautions (5.5)].

Concomitant Use with Alcohol

Advise patients that substantial consumption of alcohol (e.g., 5 units or greater) in combination with ENTADFI can increase the potential for orthostatic signs and symptoms, including increase in heart rate, decrease in standing blood pressure, dizziness, and headache [see Warnings and Precautions (5.12)].

Patient Information

ENTADFI™ (en-TAD-fee)

(finasteride and tadalafil) capsules for oral use

ENTADFI is for use by men only

Read this important information before you start taking ENTADFI and each time you get a refill. There may be new information. You may also find it helpful to share this information with your partner. This information does not take the place of talking with your healthcare provider. You and your healthcare provider should talk about ENTADFI when you start taking it and at regular checkups. If you do not understand the information, or have questions, talk with your healthcare provider or pharmacist.

What Is The Most Important Information I Should Know About ENTADFI?

ENTADFI can cause your blood pressure to drop suddenly to an unsafe level if it is taken with certain other medicines. You could get dizzy, faint, or have a heart attack or stroke. Never take ENTADFI with any nitrate or guanylate cyclase stimulator medicines.

Do not take ENTADFI if you take any medicines called "nitrates." Nitrates are commonly used to treat angina. Angina is a symptom of heart disease and can cause pain in your chest, jaw, or down your arm.

- Medicines called nitrates include nitroglycerin that is found in tablets, sprays, ointments, pastes, or patches. Nitrates can also be found in other medicines such as isosorbide dinitrate or isosorbide mononitrate. Some recreational drugs called "poppers" also contain nitrates, such as amyl nitrite and butyl nitrite.

Do not take ENTADFI if you take medicines called guanylate cyclase stimulators which include:

- Riociguat (Adempas®) a medicine that treats pulmonary arterial hypertension and chronicthromboembolic pulmonary hypertension.

Ask your healthcare provider or pharmacist if you are not sure if any of your medicines are nitrates or guanylate cyclase stimulators, such as riociguat.

Do not take ENTADFI if you are a woman who is pregnant or may potentially be pregnant.

- ENTADFI may harm your unborn baby. Do not touch or handle crushed or open ENTADFI capsules (See "Who Should Not Take ENTADFI?" and "A warning about ENTADFI and pregnancy").

Tell all of your healthcare providers that you take ENTADFI. If you need emergency medical care for a heart problem, it will be important for your healthcare provider to know when you last took ENTADFI.

After taking a single capsule, the tadalafil active ingredient of ENTADFI remains in your body for more than 2 days. The active ingredient can remain longer if you have problems with your kidneys or liver, or you are taking certain other medications (see "Can Other Medicines Affect ENTADFI?").

Stop sexual activity and get medical help right away if you get symptoms such as chest pain, dizziness, or nausea during sex. Sexual activity can put an extra strain on your heart, especially if your heart is already weak from a heart attack or heart disease.

See also "What Are The Possible Side Effects Of ENTADFI?"

You should see your doctor regularly while taking ENTADFI. Follow your doctor's advice about when to have these checkups.

Checking for prostate cancer. Your doctor has prescribed ENTADFI for BPH and not for treatment of prostate cancer — but a man can have BPH and prostate cancer at the same time. Your doctor may continue checking for prostate cancer while you take ENTADFI.

About Prostate-Specific Antigen (PSA). Your doctor may have done a blood test called PSA for the screening of prostate cancer. Because ENTADFI decreases PSA levels, you should tell your doctor(s) that you are taking ENTADFI. Changes in PSA levels will need to be evaluated by your doctor(s). Any increase in follow-up PSA levels from their lowest point may signal the presence of prostate cancer and should be evaluated, even if the test results are still within the normal range. You should also tell your doctor if you have not been taking ENTADFI as prescribed because this may affect the PSA test results. For more information, talk to your doctor.

What Is ENTADFI?

ENTADFI is a prescription medicine taken by mouth for the treatment of men with symptoms of benign prostatic hyperplasia (BPH).

BPH is a condition that happens in men, where the prostate gland enlarges which can cause urinary symptoms.

Who Should NOT Take ENTADFI?

ENTADFI is for use by MEN only.

Do not take ENTADFI if you:

- are a woman who is pregnant or may potentially be pregnant. ENTADFI may harm your unborn baby. Do not touch or handle crushed or open ENTADFI capsules (see "A warning about ENTADFI and pregnancy").
- take any medicines called "nitrates".
- use recreational drugs called "poppers" like amyl nitrite and butyl nitrite. (See "What Is The Most Important Information I Should Know About ENTADFI?")
- take any medicines called guanylate cyclase stimulators, such as riociguat.
- are allergic to ENTADFI or ADCIRCA®, or any of its ingredients. See the end of this leaflet for a complete list of ingredients in ENTADFI. Symptoms of an allergic reaction may include:

- rash

- hives

- swelling of the lips, tongue, or throat

- difficulty breathing or swallowing

Call your healthcare provider or get help right away if you have any of the symptoms of an allergic reaction listed above.

A Warning About ENTADFI and pregnancy:

Women who are or may potentially be pregnant must not use ENTADFI. They should also not handle crushed or open capsules of ENTADFI.

If a woman who is pregnant with a male baby absorbs finasteride, one of the active ingredients in ENTADFI, after oral use or through the skin, it may cause the male baby to be born with abnormalities of the sex organs. If a woman who is pregnant comes into contact with the active ingredient in ENTADFI, a doctor should be consulted.

What Should I Tell My Healthcare Provider Before Taking ENTADFI?

ENTADFI is not right for everyone. Only your healthcare provider and you can decide if ENTADFI is right for you. Before taking ENTADFI, tell your healthcare provider about all your medical problems, including if you:

- have heart problems such as angina, heart failure, irregular heartbeats, or have had a heart attack.
- have pulmonary hypertension
- have low blood pressure or have high blood pressure that is not controlled
- have had a stroke
- have liver problems
- have kidney problems or require dialysis
- have retinitis pigmentosa, a rare genetic (runs in families) eye disease
- have ever had severe vision loss, including a condition called NAION
- have stomach ulcers
- have a bleeding problem
- have a deformed penis shape or Peyronie's disease
- have had an erection that lasted more than 4 hours
- have blood cell problems such as sickle cell anemia, multiple myeloma, or leukemia

Can Other Medicines Affect ENTADFI?

Tell your healthcare provider about all the medicines you take including prescription and non-prescription medicines, vitamins, and herbal supplements. ENTADFI and other medicines may affect each other. Always check with your healthcare provider before starting or stopping any medicines. Especially tell your healthcare provider if you take any of the following*:

- medicines called nitrates (see "What Is The Most Important Information I Should Know About ENTADFI?")
- medicines called guanylate cyclase stimulators, such as riociguat (Adempas®), used to treat pulmonary hypertension
- medicines called alpha blockers. These include Hytrin® (terazosin HCl), Flomax® (tamsulosin HCl), Cardura® (doxazosin mesylate), Minipress® (prazosin HCl), Uroxatral® (alfuzosin HCl), Jalyn® (dutasteride and tamsulosin HCl) or Rapaflo® (silodosin). Alpha-blockers are sometimes prescribed for prostate problems or high blood pressure. If ENTADFI is taken with certain alpha blockers, your blood pressure could suddenly drop. You could get dizzy or faint.
- medicines to treat high blood pressure (hypertension)
- medicines called HIV protease inhibitors, such as ritonavir (Norvir®, Kaletra®)
- some types of oral antifungals such as ketoconazole (Nizoral®), itraconazole (Sporanox®)
- some types of antibiotics such as clarithromycin (Biaxin®), telithromycin (Ketek®), erythromycin (several brand names exist. Please consult your healthcare provider to determine if you are taking this medicine).
- medicines or treatments for ED.
- Tadalafil is also marketed as ADCIRCA for the treatment of pulmonary arterial hypertension. Do not take both ENTADFI and ADCIRCA. Do not take sildenafil citrate (Revatio®) with ENTADFI.

How Should I Take ENTADFI?

- Take ENTADFI exactly as your healthcare provider prescribes it.
- ENTADFI should be taken without food.
- If you take too much ENTADFI, call your healthcare provider or emergency room right away.
- Do not take ENTADFI more than one time each day.
- Take one ENTADFI capsule every day at about the same time of day.
- If you miss a dose, you may take it when you remember but do not take more than one dose per day.
- Do not share ENTADFI with anyone else; it was prescribed only for you.

What Should I Avoid While Taking ENTADFI?

- Do not use erectile dysfunction (ED) medicines or ED treatments while taking ENTADFI (unless you discuss with your healthcare provider).
- Do not drink too much alcohol when taking ENTADFI (for example, 5 glasses of wine or 5 shots of whiskey). Drinking too much alcohol can increase your chances of getting a headache or getting dizzy, increasing your heart rate, or lowering your blood pressure.

What Are The Possible Side Effects Of ENTADFI?

See "What Is The Most Important Information I Should Know About ENTADFI?"

The most common side effects with tadalafil, an active ingredient in ENTADFI, are: headache, indigestion, back pain, muscle aches, flushing, and stuffy or runny nose. These side effects usually go away after a few hours. Men who get back pain and muscle aches usually get it 12 to 24 hours after taking ENTADFI. Back pain and muscle aches usually go away within 2 days.

The most common side effects with finasteride monotherapy are: trouble getting or keeping an erection (impotence), decrease in sex drive, decreased volume of ejaculate, ejaculation disorders, and enlarged or painful breast. You should promptly report to your doctor any changes in your breasts such as lumps, pain or nipple discharge.

Call your healthcare provider if you get any side effect that bothers you or one that does not go away.

Uncommon side effects with tadalafil, an active ingredient in ENTADFI include:

An erection that won't go away (priapism). If you get an erection that lasts more than 4 hours, get medical help right away. Priapism must be treated as soon as possible or lasting damage can happen to your penis, including the inability to have erections.

Color vision changes, such as seeing a blue tinge (shade) to objects or having difficulty telling the difference between the colors blue and green.

In rare instances, men taking PDE5 inhibitors (oral erectile dysfunction medicines, including tadalafil) reported a sudden decrease or loss of vision in one or both eyes. It is uncertain whether PDE5 inhibitors directly cause the vision loss. If you experience sudden decrease or loss of vision, stop taking PDE5 inhibitors, including ENTADFI, and call a healthcare provider right away.

Sudden loss or decrease in hearing, sometimes with ringing in the ears and dizziness, has been rarely reported in people taking PDE5 inhibitors, including tadalafil. It is not possible to determine whether these events are related directly to the PDE5 inhibitors, to other diseases or medications, to other factors, or to a combination of factors. If you experience these symptoms, stop taking ENTADFI and contact a healthcare provider right away.

The following have been reported in general use with finasteride 5 mg, an active ingredient in ENTADFI, and finasteride at lower doses:

- allergic reactions, including rash, itching, hives, and swelling of the lips, tongue, throat, and face
- rarely, some men may have testicular pain
- blood in semen
- trouble getting or keeping an erection that continued after stopping the medication
- problems with ejaculation that continued after stopping the medication
- male infertility and/or poor quality of semen. Improvement in the quality of semen has been reported after stopping the medication.
- depression
- decrease in sex drive that continued after stopping the medication
- in rare cases, male breast cancer has been reported.

These are not all the possible side effects of ENTADFI. For more information, ask your healthcare provider or pharmacist.

How Should I Store ENTADFI?

Store ENTADFI at room temperature between 59° and 86°F (15° and 30°C).

Keep ENTADFI and all medicines out of the reach of children.

Women should not handle crushed or open ENTADFI capsules when they are pregnant or may potentially be pregnant because of the possibility of absorption of finasteride and the subsequent potential risk to a male fetus.

General Information About ENTADFI:

Medicines are sometimes prescribed for conditions other than those described in patient information leaflets. Do not use ENTADFI for a condition for which it was not prescribed. Do not give ENTADFI to other people, even if they have the same symptoms that you have. It may harm them.

This is a summary of the most important information about ENTADFI. If you would like more information, talk with your healthcare provider. You can ask your healthcare provider or pharmacist for information about ENTADFI that is written for health providers. For more information you can also visit www.verupharma.com, or call 1-866-936-8233.

What Are The Ingredients In ENTADFI?

Active Ingredients: finasteride and tadalafil

Inactive Ingredients: carrageenan, hypromellose, lactose monohydrate, potassium chloride, sodium starch glycolate, sodium lauryl sulfate, silicified microcrystalline cellulose, colloidal silicon dioxide, titanium dioxide, and magnesium stearate.

What is BPH?

BPH is an enlargement of the prostate gland. The prostate is located below the bladder. As the prostate enlarges, it may slowly restrict the flow of urine. This can lead to symptoms such as:

- a weak or interrupted urinary stream
- a feeling that you cannot empty your bladder completely
- a feeling of delay or hesitation when you start to urinate
- a need to urinate often, especially at night
- a feeling that you must urinate right away.

In some men, BPH can lead to serious problems, including urinary tract infections, a sudden inability to pass urine (acute urinary retention), as well as the need for surgery.

What ENTADFI does:

ENTADFI contains finasteride and tadalafil. Finasteride lowers levels of a hormone called DHT (dihydrotestosterone), which is a cause of prostate growth. Lowering DHT leads to shrinkage of the enlarged prostate gland in most men. This can lead to gradual improvement in urine flow and symptoms over the next several months. ENTADFI will help reduce the risk of developing a sudden inability to pass urine (urinary retention) and the need for surgery related to an enlarged prostate. Tadalafil may reduce BPH symptoms by inhibiting the action of an enzyme called PDE5 (phosphodiesterase 5), which relaxes the smooth muscle found in the part of the prostate that surrounds the urethra resulting in the release of the restriction to the flow of urine through the urethra. However, since each case of BPH is different, you should know that:

- Even though the prostate shrinks, you may NOT notice an improvement in urine flow or symptoms.
- You may need to take ENTADFI for up to 26 weeks to see whether it improves your symptoms.
- Therapy with ENTADFI may reduce your risk for a sudden inability to pass urine and empty your bladder and the need for surgery for an enlarged prostate.

This Patient Information has been approved by the U.S. Food and Drug Administration

Rx only

ENTADFI™ (finasteride and tadalafil) is a trademark of Veru Inc.

*The brands listed are trademarks of their respective owners and are not trademarks of Veru Inc. The makers of these brands are not affiliated with and do not endorse Veru Inc. or its products.

Revision Date: 12/2021

Marketed by: Veru Inc.
Miami, FL 33127, USA

Copyright © 2021, Veru Inc. All rights reserved.

Package Label - Bottle - 30 Capsules - ENTADFI

PRINCIPAL DISPLAY PANEL

NDC 69681-125-30

ENTADFI™

(finasteride and tadalafil) capsules 5 mg/5 mg

30 Capsules

Rx Only

Veru Inc.®

Package Label - Bottle - 90 Capsules - ENTADFI

PRINCIPAL DISPLAY PANEL

NDC 69681-125-90

ENTADFI™

(finasteride and tadalafil) capsules 5 mg/5 mg

90 Capsules

Rx Only

Veru Inc.®